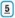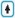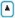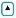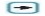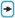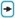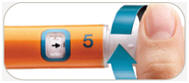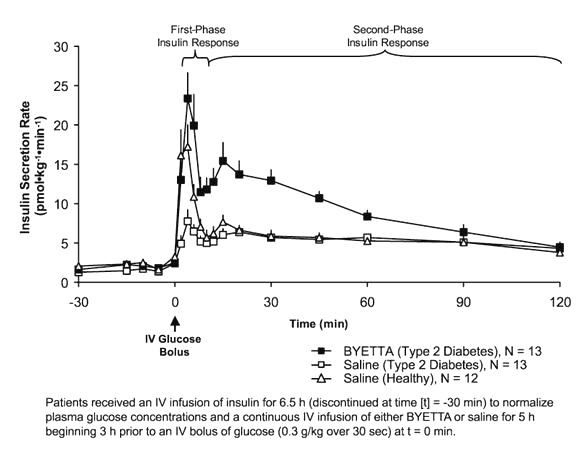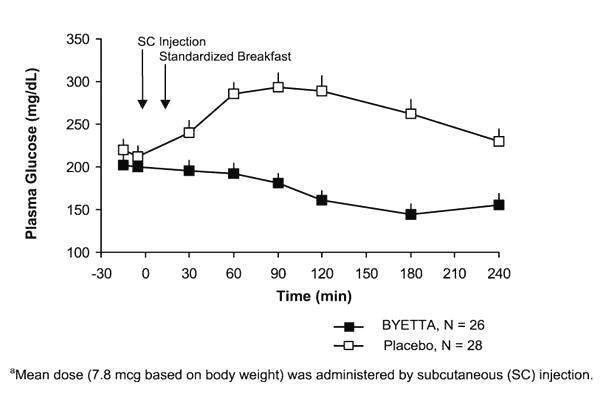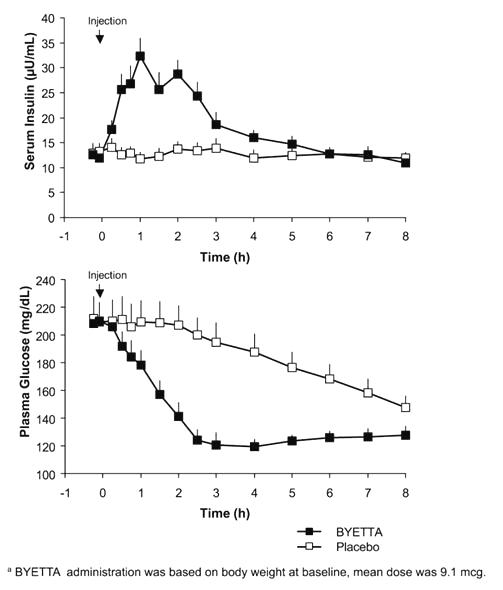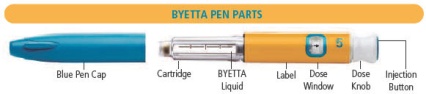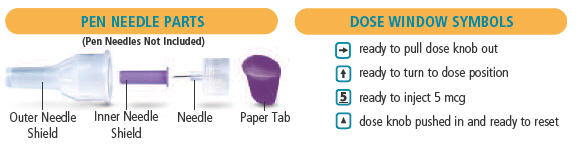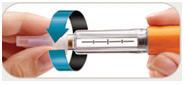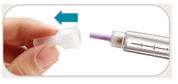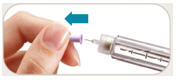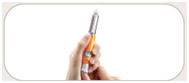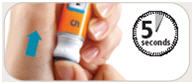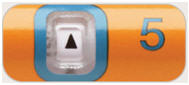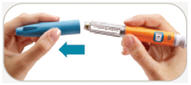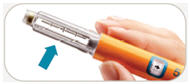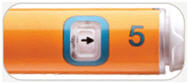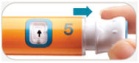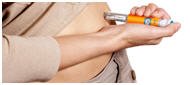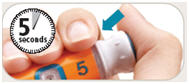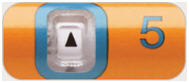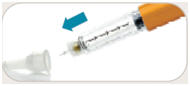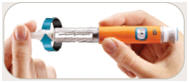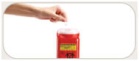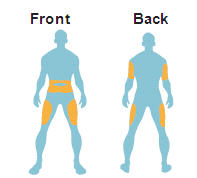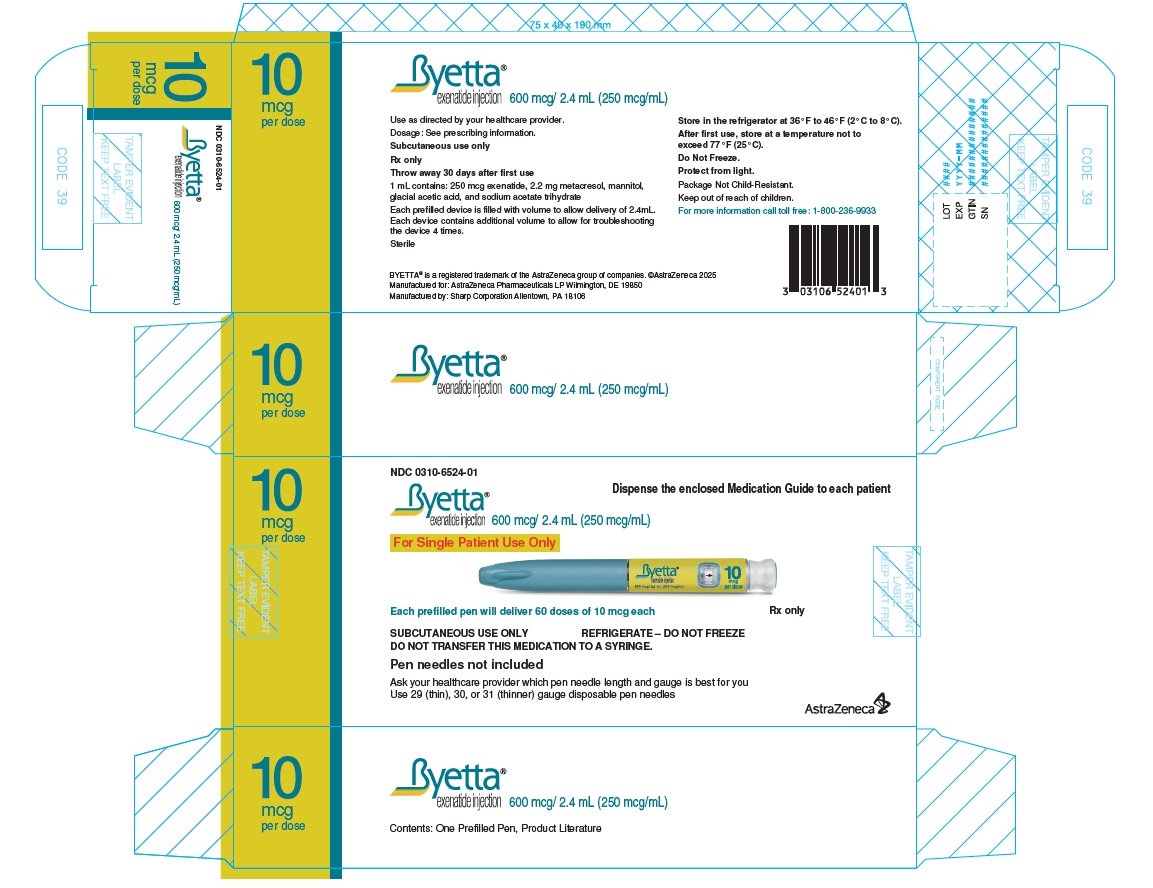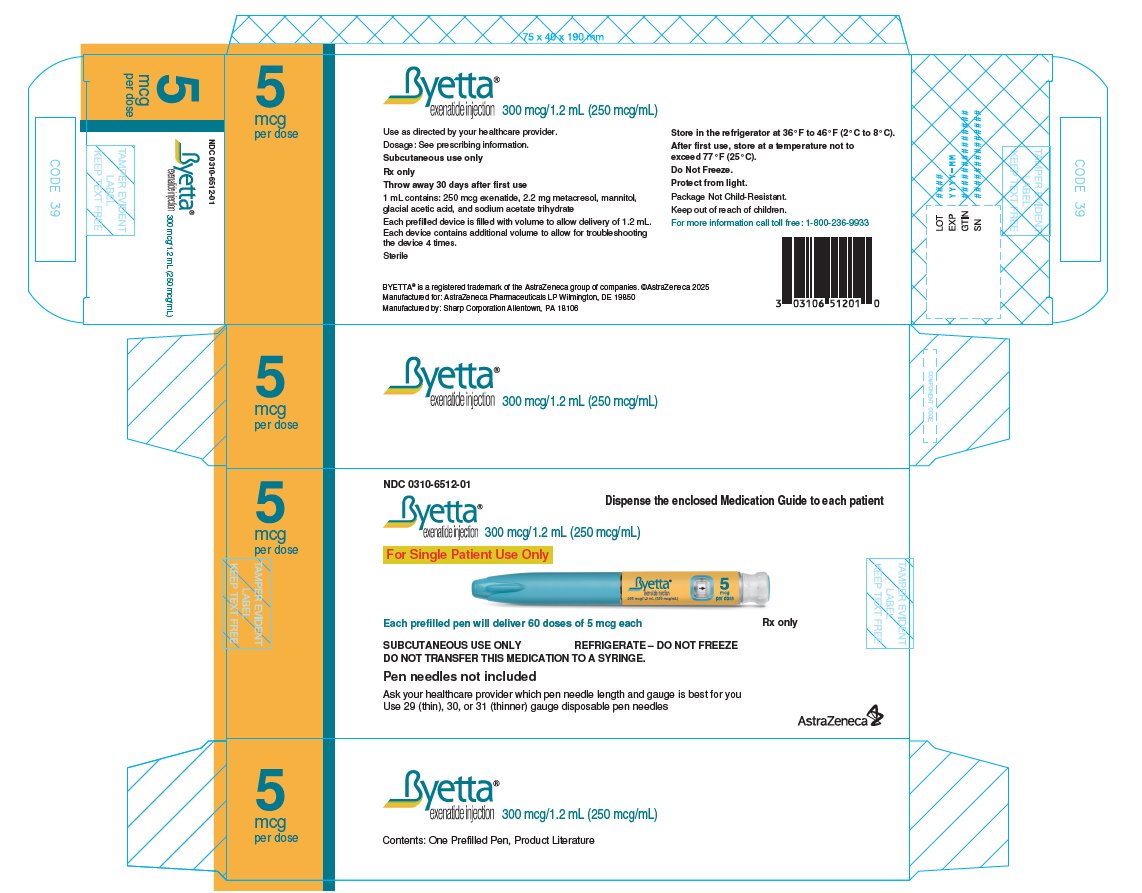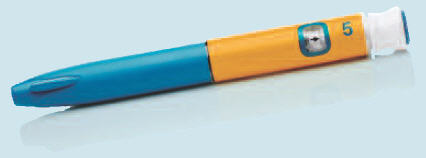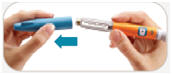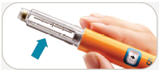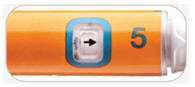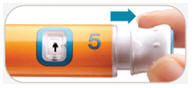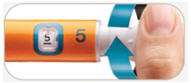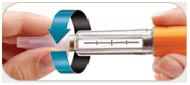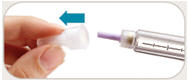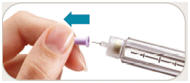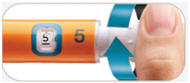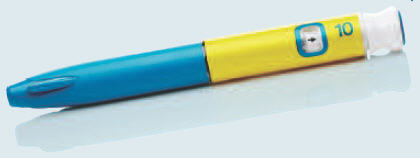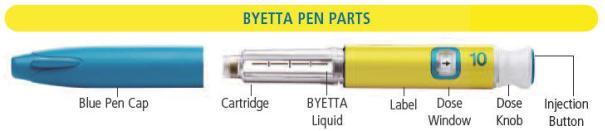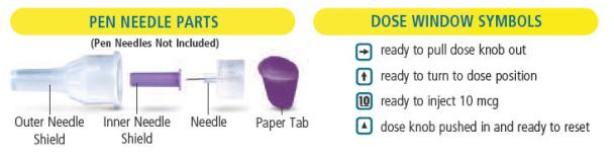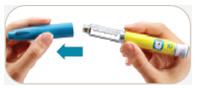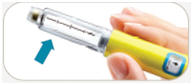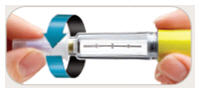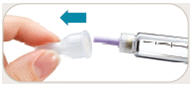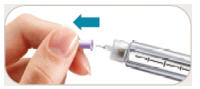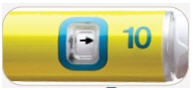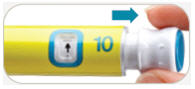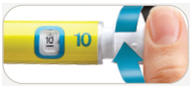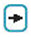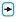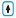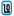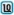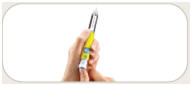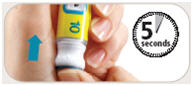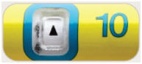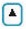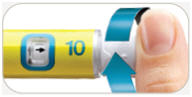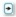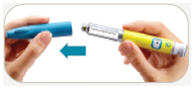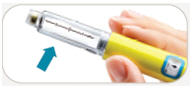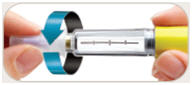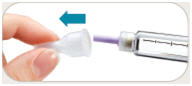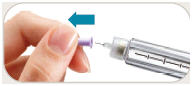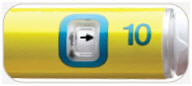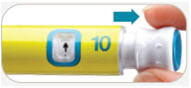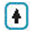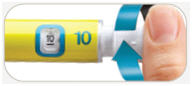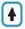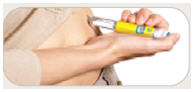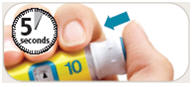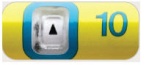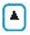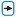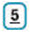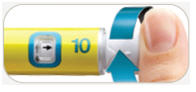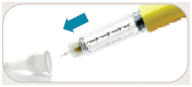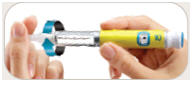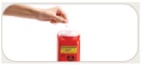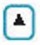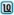 DRUG LABEL: Byetta
NDC: 0310-6512 | Form: INJECTION
Manufacturer: AstraZeneca Pharmaceuticals LP
Category: prescription | Type: HUMAN PRESCRIPTION DRUG LABEL
Date: 20250902

ACTIVE INGREDIENTS: exenatide 250 ug/1 mL
INACTIVE INGREDIENTS: acetic acid; mannitol; metacresol 2.2 mg/1 mL; sodium acetate; water

HIGHLIGHTS OF PRESCRIBING INFORMATION

These highlights do not include all the information needed to use BYETTA safely and effectively. See full prescribing information for BYETTA.
BYETTA® (exenatide) injection, for subcutaneous use
Initial U.S. Approval: 2005

RECENT MAJOR CHANGES

Warnings and Precautions, Pulmonary Aspiration During General Anesthesia or Deep Sedation (5.10) 11/2024

1 INDICATIONS AND USAGE

BYETTA (exenatide) is a glucagon-like peptide-1 (GLP-1) receptor agonist indicated as an adjunct to diet and exercise to improve glycemic control in adults with type 2 diabetes mellitus. (1, 14)

Limitations of Use

- Coadministration with other exenatide-containing products is not recommended (1).

2 DOSAGE AND ADMINISTRATION

- Inject subcutaneously within 60 minutes prior to morning and evening meals (or before the two main meals of the day, approximately 6 hours or more apart). (2.1)
- Initiate at 5 mcg per dose twice daily; increase to 10 mcg twice daily after 1 month based on clinical response. (2.1)

3 DOSAGE FORMS AND STRENGTHS

BYETTA injection is supplied as:

- 5 mcg per dose, in a single patient use prefilled pen containing 300 mcg/1.2 mL (250 mcg/mL), 60 doses.
- 10 mcg per dose, in a single patient use prefilled pen containing 600 mcg/2.4 mL (250 mcg/mL), 60 doses.

4 CONTRAINDICATIONS

- History of severe hypersensitivity to exenatide or any of the excipients in BYETTA. (4)
- History of drug-induced immune-mediated thrombocytopenia from exenatide products. (4)

5 WARNINGS AND PRECAUTIONS

- Acute Pancreatitis: Has been observed in patients treated with GLP-1 receptor agonists, including BYETTA. Discontinue if pancreatitis is suspected. (5.1)
- Never share a BYETTA pen between patients, even if the needle is changed. (5.2)
- Hypoglycemia with Concomitant Use of Insulin Secretagogues or Insulin: Patients taking an insulin secretagogue or insulin may have an increased risk of hypoglycemia, including severe hypoglycemia. Reduction in the dose of insulin secretagogues or insulin may be necessary. (5.3)
- Acute Kidney Injury Due to Volume Depletion: Monitor renal function in patients reporting adverse reactions that could lead to volume depletion (5.4)
- Severe Gastrointestinal Adverse Reactions: Use has been associated with gastrointestinal adverse reactions, sometimes severe. BYETTA is not recommended in patients with severe gastroparesis. (5.5)
- Immunogenicity: Patients may develop antibodies to exenatide. If there is worsening glycemic control or failure to achieve target glycemic control, consider alternative antidiabetic therapy. (5.6)
- Hypersensitivity: Serious hypersensitivity reactions (e.g., anaphylaxis and angioedema) have been reported. Discontinue BYETTA and promptly seek medical advice. (5.7)
- Drug-induced Immune-mediated Thrombocytopenia: Serious bleeding which may be fatal has been reported. Discontinue BYETTA promptly and avoid re-exposure to exenatide. (5.8)
- Acute Gallbladder Disease: If cholelithiasis or cholecystitis are suspected, gallbladder studies are indicated. (5.9)
- Pulmonary Aspiration During General Anesthesia or Deep Sedation: Has been reported in patients receiving GLP-1 receptor agonists undergoing elective surgeries or procedures. Instruct patients to inform healthcare providers of any planned surgeries or procedures. (5.10)

6 ADVERSE REACTIONS

- Most common (≥5%) and occurring more frequently than placebo in clinical trials: nausea, hypoglycemia, vomiting, diarrhea, feeling jittery, dizziness, headache, dyspepsia, constipation, asthenia. Nausea usually decreases over time. (5.3, 6)

To report SUSPECTED ADVERSE REACTIONS, contact AstraZeneca at 1-800-236-9933 or FDA at 1-800-FDA-1088 or www.fda.gov/medwatch.

7 DRUG INTERACTIONS

- May impact absorption of orally administered medications. (7)
- Warfarin: Postmarketing reports of increased INR sometimes associated with bleeding. Monitor INR frequently until stable upon initiation or alteration of BYETTA therapy. (7)

8 USE IN SPECIFIC POPULATIONS

- Pregnancy: Use during pregnancy only if the potential benefit justifies the risk to the fetus. (8.1)

FULL PRESCRIBING INFORMATION

1 INDICATIONS AND USAGE

BYETTA is indicated as an adjunct to diet and exercise to improve glycemic control in adults with type 2 diabetes mellitus.

Limitations of Use

- BYETTA contains exenatide. Coadministration with other exenatide-containing products is not recommended.

2 DOSAGE AND ADMINISTRATION

2.1 Recommended Dosing

- Initiate BYETTA at 5 mcg administered subcutaneously twice daily at any time within the 60-minute period before the morning and evening meals (or before the two main meals of the day, approximately 6 hours or more apart). Do not administer after a meal.
- Based on clinical response, the dose of BYETTA can be increased to 10 mcg twice daily which is recommended after 1 month of therapy, in order to reduce the risk of gastrointestinal adverse reactions [see Warnings and Precautions (5.5) and Adverse Reactions (6.1)].
- Administer as a subcutaneous injection in the thigh, abdomen, or upper arm.
- Rotate injections sites with each dose. Do not use the same site for each injection.
- Inspect visually for particulate matter and discoloration. Only use BYETTA if the solution appears clear, colorless, and contains no particles.
- When using BYETTA with insulin, administer as separate injections and never mix. It is acceptable to inject BYETTA and insulin in the same body region, but the injections should not be adjacent to each other.
- If a dose is missed, resume the treatment regimen as prescribed with the next scheduled dose.

3 DOSAGE FORMS AND STRENGTHS

BYETTA injection is a clear, colorless solution of exenatide supplied as follows:

- 5 mcg per dose in a single-patient-use prefilled pen containing 300 mcg/1.2 mL (250 mcg/mL), 60 doses.
- 10 mcg per dose in a single-patient-use prefilled pen containing 600 mcg/2.4 mL (250 mcg/mL), 60 doses.

4 CONTRAINDICATIONS

BYETTA is contraindicated in patients with:

- A prior severe hypersensitivity reaction to exenatide or to any of the excipients in BYETTA. Serious hypersensitivity reactions including anaphylaxis and angioedema have been reported with BYETTA [see Warnings and Precautions (5.7)].
- A history of drug-induced immune-mediated thrombocytopenia from exenatide products. Serious bleeding, which may be fatal, from drug-induced immune-mediated thrombocytopenia has been reported with exenatide use [see Warnings and Precautions (5.8)].

5 WARNINGS AND PRECAUTIONS

5.1 Acute Pancreatitis

Acute pancreatitis, including fatal and non-fatal hemorrhagic or necrotizing pancreatitis, has been observed in patients treated with glucagon-like peptide-1 (GLP-1) receptor agonists, including BYETTA [see Adverse Reactions (6.2)]. After initiation of BYETTA, observe patients carefully for signs and symptoms of pancreatitis (including persistent severe abdominal pain, sometimes radiating to the back and which may or may not be accompanied by vomiting). If pancreatitis is suspected, discontinue BYETTA and initiate appropriate management.

5.2 Never Share a BYETTA Pen Between Patients

BYETTA pens must never be shared between patients, even if the needle is changed. Pen-sharing poses a risk for transmission of blood-borne pathogens.

5.3 Hypoglycemia with Concomitant Use of Insulin Secretagogues or Insulin

Patients receiving BYETTA in combination with an insulin secretagogue (e.g., sulfonylurea) or insulin may have an increased risk of hypoglycemia including severe hypoglycemia [see Adverse Reactions (6) and Drug Interactions (7)].

The risk of hypoglycemia may be lowered by a reduction in the dose of sulfonylurea (or other concomitantly administered insulin secretagogue) or insulin. Inform patients using these concomitant medications of the risk of hypoglycemia and educate them on the signs and symptoms of hypoglycemia.

5.4 Acute Kidney Injury Due to Volume Depletion

There have been postmarketing reports of acute kidney injury, in some cases requiring hemodialysis, in patients treated with GLP-1 receptor agonists, BYETTA [see Adverse Reactions (6.2)]. The majority of the reported events occurred in patients who experienced gastrointestinal reactions leading to dehydration such as nausea, vomiting, or diarrhea [see Adverse Reactions (6)]. Monitor renal function in patients reporting adverse reactions to BYETTA that could lead to volume depletion, especially during dosage initiation and escalation of BYETTA.

BYETTA is not recommended in patients with severe renal impairment (creatinine clearance <30 mL/min) or end-stage renal disease and should be used with caution in patients with renal transplantation [see Use in Specific Populations (8.6)].

5.5 Severe Gastrointestinal Adverse Reactions

Use of GLP-1 receptor agonists, including BYETTA, has been associated with gastrointestinal adverse reactions, sometimes severe [see Adverse Reactions (6)]. BYETTA is not recommended in patients with severe gastroparesis.

5.6 Immunogenicity

Patients may develop antibodies to exenatide following treatment with BYETTA. Antibody levels were measured in 90% of subjects in the 30-week, 24-week, and 16-week placebo-controlled studies and the 30-week comparator-controlled study of BYETTA. In 3%, 4%, 1%, and 1% of these patients, respectively, antibody formation was associated with an attenuated glycemic response. If there is worsening glycemic control or failure to achieve targeted glycemic control, alternative antidiabetic therapy should be considered [see Adverse Reactions (6.1)].

5.7 Hypersensitivity

There have been postmarketing reports of serious hypersensitivity reactions (e.g., anaphylaxis and angioedema) in patients treated with BYETTA. If a hypersensitivity reaction occurs, the patient should discontinue BYETTA and other suspect medications and promptly seek medical advice. Inform and closely monitor patients with a history of anaphylaxis or angioedema with another GLP-1 receptor agonist for allergic reactions, because it is unknown whether such patients will be predisposed to anaphylaxis with BYETTA [see Adverse Reactions (6.2)].

5.8 Drug-Induced Thrombocytopenia

Serious bleeding, which may be fatal, from drug-induced immune-mediated thrombocytopenia has been reported in the postmarketing setting with exenatide use. Drug-induced thrombocytopenia is an immune-mediated reaction, with exenatide-dependent anti-platelet antibodies. In the presence of exenatide, these antibodies cause platelet destruction. If drug-induced thrombocytopenia is suspected, discontinue BYETTA immediately and do not re-expose the patient to exenatide [see Adverse Reactions (6.2)].

5.9 Acute Gallbladder Disease

Acute events of gallbladder disease such as cholelithiasis or cholecystitis have been reported in GLP-1 receptor agonist trials and postmarketing. In a clinical study with exenatide, 1.9% of exenatide-treated patients and 1.4% of placebo-treated patients reported an acute event of gallbladder disease, such as cholelithiasis or cholecystitis. If cholelithiasis is suspected, gallbladder studies and appropriate clinical follow-up are indicated.

5.10 Pulmonary Aspiration During General Anesthesia or Deep Sedation

BYETTA delays gastric emptying [see Clinical Pharmacology (12.2)]. There have been rare postmarketing reports of pulmonary aspiration in patients receiving GLP-1 receptor agonists undergoing elective surgeries or procedures requiring general anesthesia or deep sedation who had residual gastric contents despite reported adherence to preoperative fasting recommendations.

Available data are insufficient to inform recommendations to mitigate the risk of pulmonary aspiration during general anesthesia or deep sedation in patients taking BYETTA, including whether modifying preoperative fasting recommendations or temporarily discontinuing BYETTA could reduce the incidence of retained gastric contents. Instruct patients to inform healthcare providers prior to any planned surgeries or procedures if they are taking BYETTA.

6 ADVERSE REACTIONS

The following serious adverse reactions are described below or elsewhere in the prescribing information:

- Acute Pancreatitis [see Warnings and Precautions (5.1)]
- Never Share a BYETTA Pen Between Patients [see Warnings and Precautions (5.2)]
- Hypoglycemia with Concomitant Use of Insulin Secretagogues or Insulin [see Warnings and Precautions (5.3)]
- Acute Kidney Injury Due to Volume Depletion [see Warnings and Precautions (5.4)]
- Severe Gastrointestinal Adverse Reactions [see Warnings and Precautions (5.5)]
- Immunogenicity [see Warnings and Precautions (5.6)]
- Hypersensitivity [see Warnings and Precautions (5.7)]
- Drug-Induced Thrombocytopenia [see Warnings and Precautions (5.8)]
- Acute Gallbladder Disease [see Warnings and Precautions (5.9)]
- Pulmonary Aspiration During General Anesthesia or Deep Sedation [see Warnings and Precautions (5.10)]

6.1 Clinical Trial Experience

Because clinical trials are conducted under widely varying conditions, adverse reaction rates observed in the clinical trials of a drug cannot be directly compared to rates in the clinical trials of another drug and may not reflect the rates observed in practice.

Hypoglycemia

Table 1 summarizes the incidence and rate of hypoglycemia with BYETTA in six placebo-controlled clinical trials.

Table 1: Incidence (%) and Rate of Hypoglycemia when BYETTA was used as Monotherapy or with Concomitant Antidiabetic Therapy in Six Placebo-Controlled Clinical Trials [A hypoglycemic episode was recorded if a patient reported symptoms of hypoglycemia with or without a blood glucose value consistent with hypoglycemia. Severe hypoglycemia was defined as an event with symptoms consistent with hypoglycemia requiring the assistance of another person and associated with either a documented blood glucose value <54 mg/dL or prompt recovery after treatment for hypoglycemia.]
 | Placebo BID | BYETTA 5 mcg BID | BYETTA 10 mcg BID
Monotherapy (24 Weeks)
N | 77 | 77 | 78
% Overall | 1.3% | 5.2% | 3.8%
Rate (episodes/patient-year) | 0.03 | 0.21 | 0.52
% Severe | 0.0% | 0.0% | 0.0%
With Metformin (30 Weeks)
N | 113 | 110 | 113
% Overall | 5.3% | 4.5% | 5.3%
Rate (episodes/patient-year) | 0.12 | 0.13 | 0.12
% Severe | 0.0% | 0.0% | 0.0%
With a Sulfonylurea (30 Weeks)
N | 123 | 125 | 129
% Overall | 3.3% | 14.4% | 35.7%
Rate (episodes/patient-year) | 0.07 | 0.64 | 1.61
% Severe | 0.0% | 0.0% | 0.0%
With Metformin and a Sulfonylurea (30 Weeks)
N | 247 | 245 | 241
% Overall | 12.6% | 19.2% | 27.8%
Rate (episodes/patient-year) | 0.58 | 0.78 | 1.71
% Severe | 0.0% | 0.4% | 0.0%
With a Thiazolidinedione (16 Weeks)
N | 112 | not evaluated | 121
% Overall | 7.1% | not evaluated | 10.7%
Rate (episodes/patient-years) | 0.56 | not evaluated | 0.98
% Severe | 0.0% | not evaluated | 0.0%
With Insulin Glargine with or without Metformin and/or Thiazolidinedione (30 Weeks) [When BYETTA was initiated in combination with insulin glargine, the dose of insulin glargine was decreased by 20% in patients with an HbA1c ≤8.0% to minimize the risk of hypoglycemia. See Table 9 for insulin dose titration algorithm.]
N | 122 | not evaluated | 137
% Overall | 29.5% | not evaluated | 24.8%
Rate (episodes/patient-years) | 1.58 | not evaluated | 1.61
% Severe | 0.8% | not evaluated | 0.0%
N = number of Intent-to-Treat subjects in each treatment group.

Immunogenicity

Antibodies were assessed in 90% of subjects in the 30-week, 24-week, and 16-week studies of BYETTA. In the 30-week controlled trials of BYETTA add-on to metformin and/or sulfonylurea, antibodies were assessed at 2- to 6-week intervals. The mean antibody titer peaked at Week 6 and was reduced by 55% by Week 30. Three hundred and sixty patients (38%) had low titer antibodies (<625) to exenatide at 30 weeks. The level of glycemic control (HbA1c) in these patients was generally comparable to that observed in the 534 patients (56%) without antibody titers. An additional 59 patients (6%) had higher titer antibodies (≥625) at 30 weeks. Of these patients, 32 (3% overall) had an attenuated glycemic response to BYETTA; the remaining 27 (3% overall) had a glycemic response comparable to that of patients without antibodies.

In the 16-week trial of BYETTA add-on to thiazolidinediones, with or without metformin, 36 patients (31%) had low titer antibodies to exenatide at 16 weeks. The level of glycemic control in these patients was generally comparable to that observed in the 69 patients (60%) without antibody titer. An additional 10 patients (9%) had higher titer antibodies at 16 weeks. Of these patients, 4 (4% overall) had an attenuated glycemic response to BYETTA; the remaining 6 (5% overall) had a glycemic response comparable to that of patients without antibodies.

In the 24-week trial of BYETTA used as monotherapy, 40 patients (28%) had low titer antibodies to exenatide at 24 weeks. The level of glycemic control in these patients was generally comparable to that observed in the 101 patients (70%) without antibody titers. An additional 3 patients (2%) had higher titer antibodies at 24 weeks. Of these patients, 1 (1% overall) had an attenuated glycemic response to BYETTA; the remaining 2 (1% overall) had a glycemic response comparable to that of patients without antibodies.

Antibodies to exenatide were not assessed in the 30-week placebo-controlled trial of BYETTA used in combination with insulin glargine.

In the 30-week comparator-controlled trial of BYETTA used in combination with insulin glargine and metformin, 60 patients (20%) had low titer antibodies to exenatide at 30 weeks. The level of glycemic control in these patients was generally comparable to that observed in the 234 patients (77%) without antibody titers. An additional 10 patients (3%) had higher titer antibodies at 30 weeks. Of these patients, 2 (1% overall) had an attenuated glycemic response to BYETTA; the remaining 8 (3% overall) had a glycemic response comparable to that of patients without antibodies.

Two hundred and ten patients with antibodies to exenatide in the BYETTA clinical trials were tested for the presence of cross-reactive antibodies to GLP-1 and/or glucagon. No treatment-emergent cross-reactive antibodies were observed across the range of titers.

Other Adverse Reactions

Monotherapy

For the 24-week placebo-controlled study of BYETTA used as a monotherapy, Table 2 summarizes adverse reactions (excluding hypoglycemia) occurring with an incidence ≥2% and occurring more frequently in BYETTA-treated patients compared with placebo-treated patients.

Table 2: Treatment-Emergent Adverse Reactions ≥2% Incidence with BYETTA used as Monotherapy (excluding Hypoglycemia) [In a 24-week placebo-controlled trial.]
Monotherapy | Placebo BID N=77 % | All BYETTA BID N=155 %
Nausea | 0 | 8
Vomiting | 0 | 4
Dyspepsia | 0 | 3
BID = twice daily.

Adverse reactions reported in ≥1.0% to <2.0% of patients receiving BYETTA and reported more frequently than with placebo included decreased appetite, diarrhea, and dizziness. The most frequently reported adverse reaction associated with BYETTA, nausea, occurred in a dose-dependent fashion.

Two of the 155 patients treated with BYETTA withdrew due to adverse reactions of headache and nausea. No placebo-treated patients withdrew due to adverse reactions.

Cholelithiasis and cholecystitis

In a clinical study with exenatide, 1.9% of exenatide-treated patients and 1.4% of placebo-treated patients reported an acute event of gallbladder disease, such as cholelithiasis or cholecystitis.

Combination Therapy

Add-On to Metformin and/or Sulfonylurea

In the three 30-week controlled trials of BYETTA add-on to metformin and/or sulfonylurea, adverse reactions (excluding hypoglycemia) with an incidence ≥2% and occurring more frequently in BYETTA-treated patients compared with placebo-treated patients are summarized in Table 3.

Table 3: Treatment-Emergent Adverse Reactions ≥2% Incidence and Greater Incidence with BYETTA Treatment used with Metformin and/or a Sulfonylurea (excluding Hypoglycemia) [In three 30-week placebo-controlled clinical trials.]
 | Placebo BID N=483 % | All BYETTA BID N=963 %
Nausea | 18 | 44
Vomiting | 4 | 13
Diarrhea | 6 | 13
Feeling Jittery | 4 | 9
Dizziness | 6 | 9
Headache | 6 | 9
Dyspepsia | 3 | 6
Asthenia | 2 | 4
Gastroesophageal Reflux Disease | 1 | 3
Hyperhidrosis | 1 | 3
BID = twice daily

Adverse reactions reported in ≥1.0% to <2.0% of patients receiving BYETTA and reported more frequently than with placebo included decreased appetite. Nausea was the most frequently reported adverse reaction and occurred in a dose-dependent fashion. With continued therapy, the frequency and severity decreased over time in most of the patients who initially experienced nausea. Patients in the long-term uncontrolled open-label extension studies at 52 weeks reported no new types of adverse reactions than those observed in the 30-week controlled trials.

The most common adverse reactions leading to withdrawal for BYETTA-treated patients were nausea (3% of patients) and vomiting (1%). For placebo-treated patients, <1% withdrew due to nausea and none due to vomiting.

Add-On to Thiazolidinedione with or without Metformin

For the 16-week placebo-controlled study of BYETTA add-on to a thiazolidinedione, with or without metformin, Table 4 summarizes the adverse reactions (excluding hypoglycemia) with an incidence of ≥2% and occurring more frequently in BYETTA-treated patients compared with placebo-treated patients.

Table 4: Treatment-Emergent Adverse Reactions ≥2% Incidence with BYETTA used with a Thiazolidinedione (TZD), with or without Metformin (MET) (excluding Hypoglycemia) [In a 16-week placebo-controlled clinical trial.]
With a TZD or TZD/MET | Placebo N=112 % | All BYETTA BID N=121 %
Nausea | 15 | 40
Vomiting | 1 | 13
Dyspepsia | 1 | 7
Diarrhea | 3 | 6
Gastroesophageal Reflux Disease | 0 | 3
BID = twice daily.

Adverse reactions reported in ≥1.0% to <2.0% of patients receiving BYETTA and reported more frequently than with placebo included decreased appetite. Chills (n=4) and injection-site reactions (n=2) occurred only in BYETTA-treated patients. The two patients who reported an injection-site reaction had high titers of antibodies to exenatide. Two serious adverse events (chest pain and chronic hypersensitivity pneumonitis) were reported in the BYETTA arm. No serious adverse events were reported in the placebo arm.

The most common adverse reactions leading to withdrawal for BYETTA-treated patients were nausea (9%) and vomiting (5%). For placebo-treated patients, <1% withdrew due to nausea.

Add-On to Insulin Glargine with or without Metformin and/or Thiazolidinedione (Placebo-Controlled)

For the 30-week placebo-controlled study of BYETTA as add-on to insulin glargine with or without oral antihyperglycemic medications, Table 5 summarizes adverse reactions (excluding hypoglycemia) occurring with an incidence ≥2% and occurring more frequently in BYETTA-treated patients compared with placebo-treated patients.

Table 5: Treatment-Emergent Adverse Reactions ≥2% Incidence with BYETTA used with Insulin Glargine with or without Oral Antihyperglycemic Medications (excluding Hypoglycemia) [In a 30-week placebo-controlled clinical trial.]
With Insulin Glargine | Placebo N=122 % | All BYETTA BID N=137 %
Nausea | 8 | 41
Vomiting | 4 | 18
Diarrhea | 8 | 18
Headache | 4 | 14
Constipation | 2 | 10
Dyspepsia | 2 | 7
Asthenia | 1 | 5
Abdominal Distension | 1 | 4
Decreased Appetite | 0 | 3
Flatulence | 1 | 2
Gastroesophageal Reflux Disease | 1 | 2
BID = twice daily.

The most frequently reported adverse reactions leading to withdrawal for BYETTA-treated patients were nausea (5.1%) and vomiting (2.9%). No placebo-treated patients withdrew due to nausea or vomiting.

6.2 Postmarketing Experience

The following additional adverse reactions have been reported during post approval use of BYETTA or other formulations of exenatide. Because these events are reported voluntarily from a population of uncertain size, it is generally not possible to reliably estimate their frequency or establish a causal relationship to drug exposure.

Blood: Drug induced thrombocytopenia.

Drug Interactions: International normalized ratio (INR) increased with concomitant warfarin use sometimes associated with bleeding [see Drug Interactions (7)].

Gastrointestinal: Nausea, vomiting, and/or diarrhea resulting in dehydration; abdominal distension, abdominal pain, eructation, constipation, flatulence, ileus, acute pancreatitis, hemorrhagic and necrotizing pancreatitis sometimes resulting in death

Hepatobiliary: Cholecystitis, cholelithiasis requiring cholecystectomy.

Hypersensitivity: Injection-site reactions, generalized pruritus and/or urticaria, macular or papular rash, angioedema, anaphylactic reaction.

Neurologic: Dysgeusia, somnolence, dysesthesia.

Pulmonary: Pulmonary aspiration has occurred in patients receiving GLP-1 receptor agonists undergoing elective surgeries or procedures requiring general anesthesia or deep sedation.

Renal: Altered renal function, including increased serum creatinine, renal impairment, worsened chronic renal failure or acute renal failure (sometimes requiring hemodialysis), kidney transplant, and kidney transplant dysfunction.

Skin and Subcutaneous Tissue: Alopecia.

7 DRUG INTERACTIONS

Generic Section

Table 6: Clinically Relevant Interactions with BYETTA
Concomitant Use of Insulin Secretagogues or Insulin
Clinical Impact | Exenatide promotes insulin release from pancreatic beta-cells in the presence of elevated glucose concentrations. The risk of hypoglycemia is increased when exenatide is used in combination with insulin secretagogues (e.g., sulfonylureas) or insulin [see Warnings and Precautions (5.3) and Adverse Reactions (6)].
Intervention | When initiating BYETTA, consider reducing the dose of concomitantly administered insulin secretagogue or insulin to reduce the risk of hypoglycemia.
Warfarin
Clinical Impact | In a drug interaction study, BYETTA did not have a significant effect on INR [see Clinical Pharmacology (12.3)]. There have been postmarketing reports for BYETTA of increased INR with concomitant use of warfarin, sometimes associated with bleeding [see Adverse Reactions (6.2)].
Intervention | In patients taking warfarin, the prothrombin time should be monitored more frequently after initiation or alteration of BYETTA therapy. Once a stable prothrombin time has been documented, the prothrombin time can be monitored at the intervals recommended for patients taking warfarin.
Orally Administered Drugs (e.g., acetaminophen)
Clinical Impact | Exenatide slows gastric emptying. Therefore, BYETTA has the potential to reduce the rate of absorption of orally administered drugs [see Clinical Pharmacology (12.3)].
Intervention | Use caution when administering oral medications with BYETTA where a slower rate of oral absorption may be clinically meaningful. For oral medications that are dependent on threshold concentrations for efficacy, such as contraceptives and antibiotics, patients should be advised to take those drugs at least 1 hour before BYETTA injection. If such drugs are to be administered with food, patients should be advised to take them with a meal or snack when BYETTA is not administered [see Clinical Pharmacology (12.3)].

8 USE IN SPECIFIC POPULATIONS

8.1 Pregnancy

Risk Summary

Limited data with BYETTA in pregnant women are not sufficient to determine a drug-associated risk for major birth defects or miscarriage. There are risks to the mother and fetus associated with poorly controlled diabetes in pregnancy (see Clinical Considerations). Based on animal reproduction studies, there may be risks to the fetus from exposure to BYETTA during pregnancy. BYETTA should be used during pregnancy only if the potential benefit justifies the potential risk to the fetus.

Animal reproduction studies identified increased adverse fetal and neonatal outcomes from exposure to exenatide during pregnancy and lactation in association with maternal effects. In mice, exenatide administered during gestation and lactation caused increased neonatal deaths at systemic exposure 3-times the human exposure resulting from the maximum recommended human dose (MRHD) of 20 mcg/day for BYETTA (see Data).

The estimated background risk of major birth defects is 6-10% in women with pre-gestational diabetes with an HbA1c >7 and has been reported to be as high as 20-25% in women with HbA1c >10. The estimated background risk of miscarriage for the indicated population is unknown. In the U.S. general population, the estimated background risk of major birth defects and miscarriage in clinically recognized pregnancies is 2-4% and 15-20%, respectively.

Clinical Considerations

Disease-associated maternal and/or embryofetal risk

Poorly controlled diabetes in pregnancy increases the maternal risk for diabetic ketoacidosis, preeclampsia, spontaneous abortions, preterm delivery, and delivery complications. Poorly controlled diabetes increases the fetal risk for major birth defects, stillbirth, and macrosomia related morbidity.

Data

Animal Data

In studies evaluating reproduction and development in pregnant mice and rabbits, maternal animals were administered exenatide, the active ingredient in BYETTA, by subcutaneous injection twice a day.

In pregnant mice given 6, 68, 460, or 760 mcg/kg/day exenatide during fetal organogenesis, skeletal variations associated with slowed fetal growth, including changes in number of rib pairs or vertebral ossifications sites, and wavy ribs were observed at 760 mcg/kg/day, a dose that produced maternal toxicity and yielded systemic exposure 390-times the human exposure resulting from the MRHD of BYETTA based on AUC comparison.

In pregnant rabbits given 0.2, 2, 22, 156, or 260 mcg/kg/day exenatide during fetal organogenesis, irregular fetal skeletal ossifications were observed at 2 mcg/kg/day, a dose yielding systemic exposure up to 12-times the human exposure from the MRHD of BYETTA based on AUC comparison.

In maternal mice given 6, 68, or 760 mcg/kg/day exenatide from gestation day 6 through lactation day 20 (weaning), an increased number of neonatal deaths was observed on postpartum days 2 to 4 in dams given 6 mcg/kg/day, a dose yielding a systemic exposure 3-times the human exposure from the MRHD of BYETTA based on AUC comparison.

8.2 Lactation

Risk Summary

There is no information regarding the presence of BYETTA, in human milk, the effects of BYETTA on the breastfed infant, or the effects of BYETTA on milk production. Exenatide was present in the milk of lactating mice. However, due to species-specific differences in lactation physiology, the clinical relevance of these data is not clear (see Data). The developmental and health benefits of breastfeeding should be considered along with the mother’s clinical need for BYETTA and any potential adverse effects on the breastfed child from BYETTA or from the underlying maternal condition.

Data

In lactating mice subcutaneously injected twice a day with exenatide, the concentration of exenatide in milk was up to 2.5% of the concentration in maternal plasma.

8.4 Pediatric Use

The safety and effectiveness of BYETTA have not been established in pediatric patients.

Effectiveness of BYETTA was not demonstrated in a randomized, double-blind, placebo-controlled study conducted in 120 pediatric patients (78 received BYETTA and 42 received placebo) aged 10 to 17 years with type 2 diabetes mellitus.

8.5 Geriatric Use

Population pharmacokinetic analysis of patients ranging from 22 to 73 years of age suggests that age does not influence the pharmacokinetic properties of exenatide [see Clinical Pharmacology (12.3)]. BYETTA was studied in 282 patients 65 years of age or older and in 16 patients 75 years of age or older. No differences in safety or effectiveness were observed between these patients and younger patients. Because elderly patients are more likely to have decreased renal function, care should be taken in dose selection in the elderly based on renal function.

8.6 Renal Impairment

BYETTA is not recommended for use in patients with end-stage renal disease or severe renal impairment (creatinine clearance <30 mL/min) and should be used with caution in patients with renal transplantation. In patients with end-stage renal disease receiving dialysis, single doses of BYETTA 5 mcg were not well tolerated due to gastrointestinal adverse reactions. [see Clinical Pharmacology (12.3)].

8.7 Hepatic Impairment

No pharmacokinetic study has been performed in patients with a diagnosis of acute or chronic hepatic impairment. Because exenatide is cleared primarily by the kidney, hepatic dysfunction is not expected to affect blood concentrations of exenatide [see Clinical Pharmacology (12.3)].

10 OVERDOSAGE

In a clinical study of BYETTA, three patients with type 2 diabetes each experienced a single overdose of 100 mcg SC (10 times the maximum recommended dose). Effects of the overdoses included severe nausea, severe vomiting, and rapidly declining blood glucose concentrations. One of the three patients experienced severe hypoglycemia requiring parenteral glucose administration. The three patients recovered without complication. In the event of overdose, consider contacting the Poison Help line (1-800-222-1222) or a medical toxicologist for additional overdosage management recommendations. Initiate appropriate supportive treatment according to the patient's clinical signs and symptoms.

11 DESCRIPTION

BYETTA (exenatide) is a synthetic peptide, GLP-1 receptor agonist, that was originally identified in the lizard Heloderma suspectum.

Exenatide is a 39-amino acid peptide amide. Exenatide has the empirical formula C184H282N50O60S and molecular weight of 4186.6 Daltons. The amino acid sequence for exenatide is shown below.

H-His-Gly-Glu-Gly-Thr-Phe-Thr-Ser-Asp-Leu-Ser-Lys-Gln-Met-Glu-Glu-Glu-Ala-Val-Arg-Leu-Phe-Ile-Glu-Trp-Leu-Lys-Asn-Gly-Gly-Pro-Ser-Ser-Gly-Ala-Pro-Pro-Pro-Ser-NH2

BYETTA injection is supplied for subcutaneous administration as a sterile, preserved isotonic solution in a glass cartridge that has been assembled in a pen-injector (pen). Each milliliter (mL) contains 250 micrograms (mcg) synthetic exenatide, 2.2 mg metacresol as an antimicrobial preservative, mannitol as a tonicity-adjusting agent, and glacial acetic acid and sodium acetate trihydrate in water for injection as a buffering solution at pH 4.5. Two prefilled pens are available to deliver unit doses of 5 mcg per dose or 10 mcg per dose. Each prefilled pen will deliver 60 doses to provide for 30 days of twice daily administration (BID). Each prefilled device is filled with volume to allow delivery of 1.2 mL or 2.4 mL. Each device contains additional volume to allow for troubleshooting the device 4 times.

12 CLINICAL PHARMACOLOGY

12.1 Mechanism of Action

Incretins, such as glucagon-like peptide-1 (GLP-1), enhance glucose-dependent insulin secretion and exhibit other antihyperglycemic actions following their release into the circulation from the gut. BYETTA is a GLP-1 receptor agonist that enhances glucose-dependent insulin secretion by the pancreatic beta-cell, suppresses inappropriately elevated glucagon secretion, and slows gastric emptying.

The amino acid sequence of exenatide partially overlaps that of human GLP-1. Exenatide has been shown to bind and activate the human GLP-1 receptor in vitro. This leads to an increase in both glucose-dependent synthesis of insulin, and in vivo secretion of insulin from pancreatic beta cells, by mechanisms involving cyclic AMP and/or other intracellular signaling pathways.

BYETTA improves glycemic control by reducing fasting and postprandial glucose concentrations in patients with type 2 diabetes through the actions described below.

12.2 Pharmacodynamics

Glucose-Dependent Insulin Secretion

BYETTA has acute effects on pancreatic beta-cell responsiveness to glucose leading to insulin release predominantly in the presence of elevated glucose concentrations. This insulin secretion subsides as blood glucose concentrations decrease and approach euglycemia. However, BYETTA does not impair the normal glucagon response to hypoglycemia.

First-Phase Insulin Response

In healthy individuals, robust insulin secretion occurs during the first 10 minutes following intravenous (IV) glucose administration. This secretion, known as the "first-phase insulin response," is characteristically absent in patients with type 2 diabetes. The loss of the first-phase insulin response is an early beta-cell defect in type 2 diabetes. Administration of BYETTA at therapeutic plasma concentrations restored first-phase insulin response to an IV bolus of glucose in patients with type 2 diabetes (Figure 1). Both first-phase insulin secretion and second-phase insulin secretion were significantly increased in patients with type 2 diabetes treated with BYETTA compared with saline (p<0.001 for both).

Figure 1: Mean (+SEM) Insulin Secretion Rate during Infusion of BYETTA or Saline in Patients with Type 2 Diabetes and during Infusion of Saline in Healthy Subjects

Glucagon Secretion

In patients with type 2 diabetes, BYETTA moderates glucagon secretion and lowers serum glucagon concentrations during periods of hyperglycemia. Lower glucagon concentrations lead to decreased hepatic glucose output and decreased insulin demand.

Gastric Emptying

BYETTA slows gastric emptying, thereby reducing the rate at which meal-derived glucose appears in the circulation.

Food Intake

In both animals and humans, administration of exenatide has been shown to reduce food intake.

Postprandial Glucose

In patients with type 2 diabetes, BYETTA reduces postprandial plasma glucose concentrations (Figure 2).

Figure 2: Mean (+SEM) Postprandial Plasma Glucose Concentrations on Day 1 of BYETTAa Treatment in Patients with Type 2 Diabetes Treated with Metformin, a Sulfonylurea, or Both (N=54)

Fasting Glucose

In a single-dose crossover study in patients with type 2 diabetes and fasting hyperglycemia, immediate insulin release followed injection of BYETTA. Plasma glucose concentrations were significantly reduced with BYETTA compared with placebo (Figure 3).

Figure 3: Mean (+SEM) Serum Insulin and Plasma Glucose Concentrations Following a One-Time Injection of BYETTAa or Placebo in Fasting Patients with Type 2 Diabetes (N=12)

Cardiac Electrophysiology

The effect of exenatide 10 µg subcutaneously on QTc interval was evaluated in a randomized, placebo-, and active-controlled (moxifloxacin 400 mg) crossover thorough QTc study in 62 healthy subjects. In this study with demonstrated ability to detect small effects, the upper bound of the 90% confidence interval for the largest placebo-adjusted, baseline-corrected QTc was below 10 msec. Thus, BYETTA (10 mcg single dose) was not associated with clinically meaningful prolongation of the QTc interval.

12.3 Pharmacokinetics

Absorption

Following SC administration to patients with type 2 diabetes, exenatide reaches median peak plasma concentrations in 2.1 hours. The mean peak exenatide concentration (Cmax) was 211 pg/mL and overall mean area under the time-concentration curve (AUC0-inf) was 1036 pg∙h/mL following SC administration of a 10-mcg dose of BYETTA. Exenatide exposure (AUC) increased proportionally over the therapeutic dose range of 5 to 10 mcg. The Cmax values increased less than proportionally over the same range. Similar exposure is achieved with SC administration of BYETTA in the abdomen, thigh, or upper arm.

Distribution

The mean apparent volume of distribution of exenatide following SC administration of a single dose of BYETTA is 28.3 L.

Metabolism and Elimination

Nonclinical studies have shown that exenatide is predominantly eliminated by glomerular filtration with subsequent proteolytic degradation. The mean apparent clearance of exenatide in humans is 9.1 L/hour and the mean terminal half-life is 2.4 hours. These pharmacokinetic characteristics of exenatide are independent of the dose. In most individuals, exenatide concentrations are measurable for approximately 10 hours post-dose.

Drug Interactions

Acetaminophen

When 1000 mg acetaminophen elixir was given with 10 mcg BYETTA (0 hour) and 1 hour, 2 hours, and 4 hours after BYETTA injection, acetaminophen AUCs were decreased by 21%, 23%, 24%, and 14%, respectively; Cmax was decreased by 37%, 56%, 54%, and 41%, respectively; Tmax was increased from 0.6 hour in the control period to 0.9 hour, 4.2 hours, 3.3 hours, and 1.6 hours, respectively. Acetaminophen AUC, Cmax and Tmax were not significantly changed when acetaminophen was given 1 hour before BYETTA injection.

Digoxin

Administration of repeated doses of BYETTA (10 mcg BID) 30 minutes before oral digoxin (0.25 mg once daily) decreased the Cmax of digoxin by 17% and delayed the Tmax of digoxin by approximately 2.5 hours; however, the overall steady-state pharmacokinetic exposure (e.g., AUC) of digoxin was not changed.

Lovastatin

Administration of BYETTA (10 mcg BID) 30 minutes before a single oral dose of lovastatin (40 mg) decreased the AUC and Cmax of lovastatin by approximately 40% and 28%, respectively, and delayed the Tmax by about 4 hours compared with lovastatin administered alone. In the 30-week controlled clinical trials of BYETTA, the use of BYETTA in patients already receiving HMG CoA reductase inhibitors was not associated with consistent changes in lipid profiles compared to baseline.

Lisinopril

In patients with mild to moderate hypertension stabilized on lisinopril (5-20 mg/day), BYETTA (10 mcg BID) did not alter steady-state Cmax or AUC of lisinopril. Lisinopril steady-state Tmax was delayed by 2 hours. There were no changes in 24-hour mean systolic and diastolic blood pressure.

Oral Contraceptives

The effect of BYETTA (10 mcg BID) on single and on multiple doses of a combination oral contraceptive (30 mcg ethinyl estradiol plus 150 mcg levonorgestrel) was studied in healthy female subjects. Repeated daily doses of the oral contraceptive (OC) given 30 minutes after BYETTA administration decreased the Cmax of ethinyl estradiol and levonorgestrel by 45% and 27%, respectively, and delayed the Tmax of ethinyl estradiol and levonorgestrel by 3.0 hours and 3.5 hours, respectively, as compared to the oral contraceptive administered alone. Administration of repeated daily doses of the OC one hour prior to BYETTA administration decreased the mean Cmax of ethinyl estradiol by 15% but the mean Cmax of levonorgestrel was not significantly changed as compared to when the OC was given alone. BYETTA did not alter the mean trough concentrations of levonorgestrel after repeated daily dosing of the oral contraceptive for both regimens. However, the mean trough concentration of ethinyl estradiol was increased by 20% when the OC was administered 30 minutes after BYETTA administration injection as compared to when the OC was given alone. The effect of BYETTA on OC pharmacokinetics is confounded by the possible food effect on OC in this study. Therefore, OC products should be administered at least one hour prior to BYETTA injection.

Warfarin

Administration of warfarin (25 mg) 35 minutes after repeated doses of BYETTA (5 mcg BID on Days 1-2 and 10 mcg BID on Days 3-9) in healthy volunteers delayed warfarin Tmax by approximately 2 hours. No clinically relevant effects on Cmax or AUC of S- and R-enantiomers of warfarin were observed. BYETTA did not significantly alter the pharmacodynamic properties (e.g., international normalized ratio) of warfarin [see Drug Interactions (7)].

Specific Populations

Patients with Renal Impairment

Pharmacokinetics of exenatide was studied in subjects with normal, mild, or moderate renal impairment and subjects with end-stage renal disease. In subjects with mild to moderate renal impairment (creatinine clearance 30-80 mL/min), exenatide exposure was similar to that of subjects with normal renal function. However, in subjects with end-stage renal disease receiving dialysis, mean exenatide exposure increased by 3.37-fold compared to that of subjects with normal renal function [see Use in Specific Populations (8.6)].

Patients with Hepatic Impairment

No pharmacokinetic study has been performed in patients with a diagnosis of acute or chronic hepatic impairment [see Use in Specific Populations (8.7)].

Age

Population pharmacokinetic analysis of patients ranging from 22 to 73 years of age suggests that age does not influence the pharmacokinetic properties of exenatide [see Use in Specific Population (8.5)].

Male and Female Patients

Population pharmacokinetic analysis of male and female patients suggests that gender does not influence the distribution and elimination of exenatide.

Racial or Ethnic Groups

Population pharmacokinetic analysis of samples from White, Hispanic or Latino ethnicity, Asian, and Black or African American patients suggests that race has no significant influence on the pharmacokinetics of exenatide.

Body Mass Index

Population pharmacokinetic analysis of patients with body mass indices (BMI) ≥30 kg/m^2 and <30 kg/m^2 suggests that BMI has no significant effect on the pharmacokinetics of exenatide.

13 NONCLINICAL TOXICOLOGY

13.1 Carcinogenesis, Mutagenesis, Impairment of Fertility

A 104-week carcinogenicity study was conducted in male and female rats at doses of 18, 70, or 250 mcg/kg/day administered by bolus SC injection. Benign thyroid C-cell adenomas were observed in female rats at all exenatide doses. The incidences in female rats were 8% and 5% in the two control groups and 14%, 11%, and 23% in the low-, medium-, and high-dose groups with systemic exposures of 5-, 22-, and 130-times, respectively, the human exposure resulting from the maximum recommended dose of 20 mcg/day, based on plasma area under the curve (AUC).

In a 104-week carcinogenicity study in mice at doses of 18, 70, or 250 mcg/kg/day administered by bolus SC injection, no evidence of tumors was observed at doses up to 250 mcg/kg/day, a systemic exposure up to 95-times the human exposure resulting from the maximum recommended dose of 20 mcg/day, based on AUC.

Exenatide was not mutagenic or clastogenic, with or without metabolic activation, in the Ames bacterial mutagenicity assay or chromosomal aberration assay in Chinese hamster ovary cells. Exenatide was negative in the in vivo mouse micronucleus assay.

In mouse fertility studies with SC doses of 6, 68, or 760 mcg/kg/day, males were treated for 4 weeks prior to and throughout mating, and females were treated 2 weeks prior to mating and throughout mating until gestation day 7. No adverse effect on fertility was observed at 760 mcg/kg/day, a systemic exposure 390-times the human exposure resulting from the maximum recommended dose of 20 mcg/day, based on AUC.

14 CLINICAL STUDIES

BYETTA has been studied as monotherapy and in combination with metformin, a sulfonylurea, a thiazolidinedione, a combination of metformin and a sulfonylurea, a combination of metformin and a thiazolidinedione, or in combination with insulin glargine with or without metformin and/or thiazolidinedione.

14.1 Monotherapy

In a randomized, double-blind, placebo-controlled trial of 24 weeks duration, BYETTA 5 mcg BID (n=77), BYETTA 10 mcg BID (n=78), or placebo BID (n=77) was used as monotherapy in patients with entry HbA1c ranging from 6.5% to 10%. All patients assigned to BYETTA initially received 5 mcg BID for 4 weeks. After 4 weeks, those patients either continued to receive BYETTA 5 mcg BID or had their dose increased to 10 mcg BID. Patients assigned to placebo received placebo BID throughout the trial. BYETTA or placebo was injected subcutaneously before the morning and evening meals. The majority of patients (68%) were White, 26% were West Asian, 3% were Hispanic or Latino ethnicity, 3% were Black or African American, and 0.4% were of East Asian ethnicity.

The primary endpoint was the change in HbA1c from baseline to Week 24 (or the last value at time of early discontinuation). Compared to placebo, BYETTA 5 mcg BID and 10 mcg BID resulted in statistically significant reductions in HbA1c from baseline at Week 24 (Table 7).

Table 7: Results of 24-Week Placebo-Controlled Trial of BYETTA used as Monotherapy
 | Placebo BID | BYETTA 5 mcg BID | BYETTA 10 mcg [BYETTA 5 mcg twice daily (BID) for 1 month followed by 10 mcg BID for 5 months before the morning and evening meals.] BID
Intent-to-Treat Population (N) | 77 | 77 | 78
HbA1c (%), Mean
Baseline | 7.8 | 7.9 | 7.8
Change at Week 24 [Least squares means are adjusted for screening HbA1c strata and baseline value of the dependent variable.] | −0.2 | −0.7 | −0.9
Difference from placebo (95% CI) |  | −0.5 [−0.9, −0.2] [p <0.01, treatment vs. placebo.] | −0.7 [−1.0, −0.3]
Proportion Achieving HbA1c <7% | 38% | 48% | 53%
Body Weight (kg), Mean
Baseline | 86.1 | 85.1 | 86.2
Change at Week 24 | −1.5 | −2.7 | −2.9
Difference from placebo (95% CI) |  | −1.3 [−2.3, −0.2] | −1.5 [−2.5, −0.4]
Fasting Serum Glucose [Measured using the hexokinase-based glucose method.] (mg/dL), Mean
Baseline | 159 | 166 | 155
Change at Week 24 | −5 | −17 | −19
Difference from placebo (95% CI) |  | −12 [−23.2, −1.3] | −14 [−24.5, −2.5]
BID = twice daily.

On average, there were no adverse effects of exenatide on blood pressure or lipids.

14.2 Combination Therapy with Oral Antihyperglycemic Medicines

Three 30-week, double-blind, placebo-controlled trials were conducted to evaluate the safety and efficacy of BYETTA in patients with type 2 diabetes whose glycemic control was inadequate with metformin alone, a sulfonylurea alone, or metformin in combination with a sulfonylurea. In addition, a 16-week, placebo-controlled trial was conducted where BYETTA was added to existing thiazolidinedione (pioglitazone or rosiglitazone) treatment, with or without metformin, in patients with type 2 diabetes with inadequate glycemic control.

In the 30-week trials, after a 4-week placebo lead-in period, patients were randomly assigned to receive BYETTA 5 mcg BID, BYETTA 10 mcg BID, or placebo BID before the morning and evening meals, in addition to their existing oral antidiabetic agent. All patients assigned to BYETTA initially received 5 mcg BID for 4 weeks. After 4 weeks, those patients either continued to receive BYETTA 5 mcg BID or had their dose increased to 10 mcg BID. Patients assigned to placebo received placebo BID throughout the study. A total of 1446 patients were randomized in the three 30-week trials: 991 (69%) were White, 224 (16%) were Hispanic or Latino and 174 (12%) were of Black of African American ethnicity. Mean HbA1c values at baseline for the trials ranged from 8.2% to 8.7%.

In the placebo-controlled trial of 16 weeks duration, BYETTA (n=121) or placebo (n=112) was added to existing thiazolidinedione (pioglitazone or rosiglitazone) treatment, with or without metformin. Randomization to BYETTA or placebo was stratified based on whether the patients were receiving metformin. BYETTA treatment was initiated at a dose of 5 mcg BID for 4 weeks then increased to 10 mcg BID for 12 more weeks. Patients assigned to placebo received placebo BID throughout the study. BYETTA or placebo was injected subcutaneously before the morning and evening meals. In this trial, 79% of patients were taking a thiazolidinedione and metformin and 21% were taking a thiazolidinedione alone. The majority of patients (84%) were White, 8% were Hispanic or Latino ethnicity, and 3% were of Black or African American ethnicity. The mean baseline HbA1c values were 7.9% for BYETTA and placebo.

The primary endpoint in each study was the mean change in HbA1c from baseline to study end (or early discontinuation). Table 8 summarizes the study results for the 30- and 16-week clinical trials.

Table 8: Results of 30-Week and 16-Week Placebo-Controlled Trials of BYETTA used in Combination with Oral Antidiabetic Agents
 | Placebo BID | BYETTA 5 mcg BID | BYETTA 10 mcg [BYETTA 5 mcg twice daily for 1 month followed by 10 mcg BID for 6 months for the 30-week trials or 10 mcg BID for 3 months in the 16-week trial before the morning and evening meals.] BID
 | In Combination with Metformin (30 Weeks)
Intent-to-Treat Population (N) | 113 | 110 | 113
HbA1c (%), Mean
Baseline | 8.2 | 8.3 | 8.2
Change at Week 30 [Least squares means are adjusted for baseline HbA1c strata or value, investigator site, baseline value of the dependent variable (if applicable), and background antihyperglycemic therapy (if applicable).] | −0.0 | −0.5 | −0.9
Difference from placebo (95% CI) |  | −0.5 [−0.7, −0.2] [p <0.01, treatment vs. placebo.] | −0.9 [−1.1, −0.6]
Proportion Achieving HbA1c <7% | 12% | 32% | 40%
Body Weight (kg), Mean
Baseline | 99.9 | 100.0 | 100.9
Change at Week 30 | −0.2 | −1.3 | −2.6
Difference from placebo (95% CI) |  | −1.1 [−2.2, −0.0] | −2.4 [−3.5, −1.3]
Fasting Plasma Glucose [Measured using the hexokinase-based glucose method.] (mg/dL), Mean
Baseline | 169 | 176 | 168
Change at Week 30 | +14 | −5 | −10
Difference from placebo (95% CI) |  | −20 [−32, −7] | −24 [−37, −12]
 | In Combination with a Sulfonylurea (30 Weeks)
Intent-to-Treat Population (N) | 123 | 125 | 129
HbA1c (%), Mean
Baseline | 8.7 | 8.5 | 8.6
Change at Week 30 | +0.1 | −0.5 | −0.9
Difference from placebo (95% CI) |  | −0.6 [−0.9, −0.3] | −1.0 [−1.3, −0.7]
Proportion Achieving HbA1c <7% | 10% | 25% | 36%
Body Weight (kg), Mean
Baseline | 99.1 | 94.9 | 95.2
Change at Week 30 | −0.8 | −1.1 | −1.6
Difference from placebo (95% CI) |  | −0.3 [−1.1, 0.6] | −0.9 [−1.7, −0.0]
Fasting Plasma Glucose (mg/dL), Mean
Baseline | 194 | 180 | 178
Change at Week 30 | +6 | −5 | −11
Difference from placebo (95% CI) |  | −11 [−25, 3] | −17 [−30, −3]
 | In Combination with Metformin and a Sulfonylurea (30 Weeks)
Intent-to-Treat Population (N) | 247 | 245 | 241
HbA1c (%), Mean
Baseline | 8.5 | 8.5 | 8.5
Change at Week 30 | +0.1 | −0.7 | −0.9
Difference from placebo (95% CI) |  | −0.8 [−1.0, −0.6] | −1.0 [−1.2, −0.8]
Proportion Achieving HbA1c <7% | 8% | 25% | 31%
Body Weight (kg), Mean
Baseline | 99.1 | 96.9 | 98.4
Change at Week 30 | −0.9 | −1.6 | −1.6
Difference from placebo (95% CI) |  | −0.7 [−1.2, −0.2] | −0.7 [−1.3, −0.2]
Fasting Plasma Glucose (mg/dL), Mean
Baseline | 181 | 182 | 178
Change at Week 30 | +13 | −11 | −12
Difference from placebo (95% CI) |  | −24 [−33, −15] | −25 [−34, −16]
 | In Combination with a Thiazolidinedione or a Thiazolidinedione plus Metformin (16 Weeks)
Intent-to-Treat Population (N) | 112 | Dose not studied | 121
HbA1c (%), Mean
Baseline | 7.9 | Dose not studied | 7.9
Change at Week 16 | +0.1 | Dose not studied | −0.7
Difference from placebo (95% CI) |  | Dose not studied | −0.9 [−1.1, −0.7]
Proportion Achieving HbA1c <7% | 15% | Dose not studied | 51%
Body Weight (kg), Mean
Baseline | 96.8 | Dose not studied | 97.5
Change at Week 16 | −0.0 | Dose not studied | −1.5
Difference from placebo (95% CI) |  | Dose not studied | −1.5 [−2.2, −0.7]
Fasting Serum Glucose (mg/dL), Mean
Baseline | 159 | Dose not studied | 164
Change at Week 16 | +4 | Dose not studied | −21
Difference from placebo (95% CI) |  | Dose not studied | −25 [−33, −16]
BID = twice daily.

HbA1c

The addition of BYETTA to a regimen of metformin, a sulfonylurea, or both, resulted in statistically significant reductions from baseline in HbA1c compared with patients receiving placebo added to these agents in the three controlled trials (Table 8).

In the 16-week trial of BYETTA add-on to thiazolidinediones, with or without metformin, BYETTA resulted in statistically significant reductions from baseline in HbA1c compared with patients receiving placebo (Table 8).

Postprandial Glucose

Postprandial glucose was measured after a mixed meal tolerance test in 9.5% of patients participating in the 30-week add-on to metformin, add-on to sulfonylurea, and add-on to metformin in combination with sulfonylurea clinical trials. In this pooled subset of patients, BYETTA reduced postprandial plasma glucose concentrations in a dose-dependent manner. The mean (SD) change in 2-hour postprandial glucose concentration following administration of BYETTA at Week 30 relative to baseline was −63 (65) mg/dL for 5 mcg BID (n=42), −71 (73) mg/dL for 10 mcg BID (n=52), and +11 (69) mg/dL for placebo BID (n=44).

14.3 Combination with Insulin Glargine

30-Week Placebo-Controlled Trial

A 30-week, double-blind, placebo-controlled trial was conducted to evaluate the efficacy and safety of BYETTA (n=137) versus placebo (n=122) when added to titrated insulin glargine, with or without metformin and/or thiazolidinedione, in patients with type 2 diabetes with inadequate glycemic control.

All patients assigned to BYETTA initially received 5 mcg BID for 4 weeks. After 4 weeks, those patients assigned to BYETTA had their dose increased to 10 mcg BID. Patients assigned to placebo received placebo BID throughout the trial. BYETTA or placebo was injected subcutaneously before the morning and evening meals. Patients with an HbA1c ≤8.0% decreased their prestudy dose of insulin glargine by 20% and patients with an HbA1c ≥8.1% maintained their current dose of insulin glargine. Five weeks after initiating randomized treatment, insulin doses were titrated with guidance from the investigator toward predefined fasting glucose targets according to the dose titration algorithm provided in Table 9. The majority of patients (78%) were White, 10% were American Indian or Alaska Native, 9% were Black or African American, 3% were Asian, and 0.8% were of multiple origins.

The primary endpoint was the change in HbA1c from baseline to Week 30. Compared to placebo, BYETTA 10 mcg BID resulted in statistically significant reductions in HbA1c from baseline at Week 30 (Table 9) in patients receiving titrated insulin glargine.

Table 9: 30-Week Placebo-Controlled Trial of BYETTA Used in Combination with Insulin Glargine with or without Metformin and/or Thiazolidinediones
 | Placebo BID + Titrated Insulin Glargine | BYETTA 10 mcg [BYETTA 5 mcg twice daily for 1 month followed by 10 mcg BID for 5 months for the 30-week trial.] BID + Titrated Insulin Glargine
Intent-to-Treat Population (N) | 122 | 137
HbA1c (%), Mean
Baseline | 8.5 | 8.3
Change at Week 30 [Least squares means are based on a mixed model adjusting for treatment, pooled investigator, visit, baseline HbA1c value, and treatment by visit, where subject is treated as a random effect.] | −1.0 | −1.7
Difference from placebo (95% CI) |  | −0.7 [−1.0, −0.5] [p <0.01, treatment vs. placebo.]
Proportion Achieving HbA1c <7% | 29% | 56%
Body Weight (kg), Mean
Baseline | 93.8 | 95.4
Change at Week 30 [Least squares means are based on a mixed model adjusting for treatment, pooled investigator, visit, baseline HbA1c stratum, baseline value of the dependent variable (where applicable), and treatment by visit, where subject is treated as a random effect.] | 1.0 | −1.8
Difference from placebo (95% CI) |  | −2.7 [−3.7, −1.7]
Fasting Serum Glucose [Patients in both groups titrated insulin glargine dose to achieve optimal fasting glucose concentrations.] (mg/dL), Mean
Baseline | 133 | 132
Change at Week 30 | −16 | −23
Difference from placebo (95% CI) |  | −7 [−18, 3]
BID = twice daily.

Table 10: Dosing Algorithm for Titration of Insulin Glargine [Adapted from Riddle et al. 2003.]
Fasting Plasma Glucose Values (mg/dL) | Dose Change (U)
<56 [Value for at least 1 fasting plasma glucose measurement since the last assessment.] | −4
56 to 72 | −2
73 to 99 [Based on the average of fasting plasma glucose measurements taken over the prior 3 to 7 days. The increase in the total daily dose should not have exceeded more than 10 units per day or 10% of the current total daily dose, whichever was greater.] | 0
100 to 119 | +2
120 to 139 | +4
140 to 179 | +6
≥180 | +8
Abbreviations: U = units.

30-Week Comparator-Controlled Noninferiority Trial

A 30 week, open-label, active comparator-controlled, noninferiority study was conducted to evaluate the safety and efficacy of BYETTA (n=315) versus titrated insulin lispro (n=312) on a background of optimized basal insulin glargine and metformin in patients with type 2 diabetes with inadequate glycemic control.

Following a 12-week basal insulin optimization (BIO) phase, subjects with an HbA1c >7.0% entered a 30-week intervention phase and were randomized to add either BYETTA or insulin lispro to their existing regimen of insulin glargine and metformin. Insulin glargine was titrated to a target fasting plasma glucose of 72 to 100 mg/dL.

All patients assigned to BYETTA initially received 5 mcg BID for four weeks. After four weeks, their dose was increased to 10 mcg BID. Patients in the BYETTA-treated arm with an HbA1c ≤8.0% at the end of the BIO phase decreased their insulin glargine dose by at least 10%.

All patients assigned to insulin lispro three times daily (TID) maintained their prior total daily insulin dose at baseline; however, the initial insulin lispro dose was ⅓ to ½ of the total daily insulin dose with the insulin glargine dose reduced accordingly. The insulin lispro dose was titrated based on preprandial glucose values.

The majority of patients (87%) were White, 7% were American Indian or Alaska Native, 5% were Asian, and <1% were of Black or African American ethnicity.

The primary endpoint was the change in HbA1c from baseline to Week 30. Both BYETTA 10 mcg BID and titrated lispro provided a mean reduction in HbA1c at Week 30 that met the pre-specified non-inferiority margin of 0.4%.

Table 11: 30-Week Comparator-Controlled Trial of BYETTA used in Combination with Insulin Glargine and Metformin
 | Titrated Insulin Lispro TID; +; Titrated Insulin Glargine | BYETTA 10 mcg [BYETTA 5 mcg BID for 1 month followed by 10 mcg BID for 5 months for the 30-week trial.] BID; +; Titrated Insulin Glargine
Intent-to-Treat Population (N) | 312 | 315
HbA1c (%), Mean
Baseline | 8.2 | 8.3
Change at Week 30 [Least squares means are based on a mixed model adjusting for treatment, country, prior use of sulfonylurea (yes/no), visit, corresponding baseline, and treatment by visit interaction, where subject is treated as a random effect.] [Data at 30 weeks are available from 88% and 84% of the intent-to-treat subjects in the Lispro and BYETTA groups, respectively.] | −1.1 | −1.1
Difference from Insulin Lispro (95% CI) |  | −0.0 [−0.2, 0.1]
Body Weight (kg), Mean
Baseline | 89.3 | 89.9
Change at Week 30 | 1.9 | −2.6
Difference from Insulin Lispro (95% CI) |  | −4.5 [−5.2, −3.9]
Fasting Serum Glucose [Patients titrated insulin glargine or insulin lispro dose to achieve prespecified target fasting and preprandial glucose concentrations.] (mg/dL), Mean
Baseline | 126 | 130
Change at Week 30 | 5 | −7
Difference from Insulin Lispro (95% CI) |  | −12 [−19, −4]
BID = twice daily.
TID = three times daily.

16 HOW SUPPLIED/STORAGE AND HANDLING

16.1 How Supplied

BYETTA (exenatide) Injection is a clear, colorless solution supplied as:

- 5 mcg per dose, in a single-patient-use prefilled pen containing 300 mcg/1.2 mL (250 mcg/mL), 60 doses, NDC 0310-6512-01.
- 10 mcg per dose, in a single-patient-use prefilled pen containing 600 mcg/2.4 mL (250 mcg/mL), 60 doses, NDC 0310-6524-01.

16.2 Storage and Handling

- Store BYETTA in the refrigerator at 36°F to 46°F (2°C to 8°C).
- After first use, BYETTA can be kept at a temperature not to exceed 77°F (25°C).
- Do not freeze. Do not use BYETTA if it has been frozen.
- Protect BYETTA from light.
- Discard the pen 30 days after first use, even if some drug remains in the pen.
- Use a puncture-resistant container to discard the needles. Do not reuse or share needles.

17 PATIENT COUNSELING INFORMATION

Advise the patient to read the FDA-approved patient labeling (Medication Guide and Instructions for Use).

Acute Pancreatitis

Inform patients of the potential risk for acute pancreatitis and its symptoms: severe abdominal pain that may radiate to the back, and which may or may not be accompanied by vomiting. Instruct patients to discontinue BYETTA promptly and contact their physician if pancreatitis is suspected [see Warnings and Precautions (5.1)].

Never Share a BYETTA Pen Between Patients

Advise patients that they must never share a BYETTA pen with another person, even if the needle is changed, because doing so carries a risk for transmission of blood-borne pathogens [see Warnings and Precautions (5.2)].

Hypoglycemia with Concomitant Use of Insulin Secretagogues or Insulin

Inform patients that the risk of hypoglycemia is increased when BYETTA is used in combination with an agent that induces hypoglycemia, such as a sulfonylurea or insulin. Educate patients on the signs and symptoms of hypoglycemia [see Warnings and Precautions (5.3)].

Acute Kidney Injury Due to Volume Depletion

Inform patients of the potential risk of acute kidney injury due to dehydration associated with gastrointestinal adverse reactions. Advise patients to take precautions to avoid fluid depletion. Inform patients of the signs and symptoms of acute kidney injury and instruct them to promptly report any of these signs or symptoms or persistent (or extended) nausea, vomiting, and diarrhea to their healthcare provider [see Warnings and Precautions (5.4)].

Severe Gastrointestinal Adverse Reactions

Inform patients of the potential risk of severe gastrointestinal adverse reactions. Instruct patients to contact their healthcare provider if they have severe or persistent gastrointestinal symptoms [see Warnings and Precautions (5.5)].

Drug-Induced Thrombocytopenia

Inform patients that drug-induced immune mediated thrombocytopenia has been reported during use of exenatide. Inform patients that if symptoms of thrombocytopenia occur, stop taking BYETTA and seek medical advice promptly [see Warnings and Precautions (5.8)].

Hypersensitivity Reactions

Inform patients that serious hypersensitivity reactions have been reported during postmarketing use of BYETTA. If symptoms of hypersensitivity reactions occur, instruct patients to stop taking BYETTA and seek medical advice promptly [see Warnings and Precautions (5.7)].

Acute Gallbladder Disease

Inform patients of the potential risk for cholelithiasis or cholecystitis. Instruct patients to contact their physician if cholelithiasis or cholecystitis is suspected for appropriate clinical follow-up [see Warnings and Precautions (5.9)].

Pulmonary Aspiration During General Anesthesia or Deep Sedation

Inform patients that BYETTA may cause their stomach to empty more slowly which may lead to complications with anesthesia or deep sedation during planned surgeries or procedures. Instruct patients to inform healthcare providers prior to any planned surgeries or procedures if they are taking BYETTA [see Warnings and Precautions (5.10)].

Pregnancy

Advise patients to inform their physicians if they are pregnant or intend to become pregnant.

Instructions

Instruct patients to administer BYETTA as a subcutaneous injection in the thigh, abdomen, or upper arm at any time within the 60-minute period before the morning and evening meals (or before the two main meals of the day, approximately 6 hours or more apart). Do not administer BYETTA after a meal. If a dose is missed, resume the treatment regimen as prescribed with the next scheduled dose.

Distributed by:
AstraZeneca Pharmaceuticals LP
Wilmington, DE 19850

BYETTA® is a registered trademark of the AstraZeneca group of companies.

MEDICATION GUIDE

BYETTA® (bye-A-tuh)

(exenatide)

injection, for subcutaneous use

Read this Medication Guide and the Instructions for Use that comes with BYETTA before you start using it and each time you get a refill. There may be new information. This Medication Guide does not take the place of talking with your healthcare provider about your medical condition or your treatment. If you have questions about BYETTA after reading this information, ask your healthcare provider or pharmacist.

What is the most important information I should know about BYETTA?

- Serious side effects can happen in people who take BYETTA, including inflammation of your pancreas (pancreatitis). Stop using BYETTA and call your healthcare provider right away if you have severe pain in your stomach area (abdomen) that will not go away, with or without vomiting. You may feel the pain from your abdomen to your back.

What is BYETTA?

- BYETTA is an injectable prescription medicine that is used along with diet and exercise to improve blood sugar (glucose) in adults with type 2 diabetes mellitus.
- BYETTA is not recommended for people who take exenatide or other medicines called glucagon-like peptide 1 (GLP-1) receptor agonist.
- It is not known if BYETTA is safe and effective in children.

Who should not use BYETTA?

Do not use BYETTA if:

- you have had a severe allergic reaction to exenatide or any of the other ingredients in BYETTA. See the end of this Medication Guide for a complete list of ingredients in BYETTA. See “What are the possible side effects of BYETTA?” for symptoms of a serious allergic reaction.
- you have a history of low blood platelet count from using exenatide medicines (drug-induced thrombocytopenia).

Before taking BYETTA, tell your healthcare provider about all of your medical conditions, including if you:

- have or have had problems with your pancreas.
- have severe problems with your stomach, such as delayed emptying of your stomach (gastroparesis) or problems with digesting food.
- are scheduled to have surgery or other procedures that use anesthesia or deep sleepiness (deep sedation).
- are pregnant or plan to become pregnant. It is not known if BYETTA will harm your unborn baby. Tell your healthcare provider if you become pregnant while taking BYETTA. Talk to your healthcare provider about the best way to control your blood sugar if you plan to become pregnant or while you are pregnant.
- are breastfeeding or plan to breastfeed. It is not known if BYETTA passes into your breast milk. You should talk with your healthcare provider about the best way to feed your baby while taking BYETTA.

Tell your healthcare provider about all the medicines you take, including prescription and over-the-counter medicines, vitamins, and herbal supplements. BYETTA may affect the way some medicines work and some other medicines may affect the way BYETTA works.

Before using BYETTA, talk to your healthcare provider about low blood sugar and how to manage it. Tell your healthcare provider if you are taking other medicines to treat diabetes, including insulin or sulfonylureas.

Especially tell your healthcare provider if you take:

- birth control pills that are taken by mouth (oral contraceptives). BYETTA may lower the amount of the medicine in your blood from your birth control pills and they may not work as well to prevent pregnancy. Take your birth control pills at least one hour before your injection of BYETTA. If you must take your birth control pills with food, take it with a meal or snack at a time when you do not also take BYETTA.
- antibiotics. Take antibiotic medicines at least one hour before taking BYETTA. If you must take your antibiotic with food, take it with a meal or snack at a time when you do not also take BYETTA.
- warfarin
- lovastatin

Know the medicines you take. Keep a list of them to show your healthcare provider and pharmacist when you get a new medicine.

How should I use BYETTA?

- Read the Instructions for Use that comes with BYETTA.
- Use BYETTA exactly as your healthcare provider tells you to.
- Your healthcare provider should teach you how to inject BYETTA before you use it for the first time.
- Inject your dose of BYETTA under the skin (subcutaneous injection) of your upper leg (thigh), stomach area (abdomen), or upper arm as instructed by your healthcare provider. Do not inject into a muscle (intramuscularly) or vein (intravenously).
- Inject BYETTA two times each day, at any time within 60 minutes (1 hour) before your morning and evening meals (or before the two main meals of the day, approximately 6 hours or more apart). Do not take BYETTA after your meal.
- If you miss a dose of BYETTA, skip that dose and take your next dose at the next prescribed time. Do not take an extra dose or increase the amount of your next dose to make up for a missed dose.
- Do not mix insulin and BYETTA together in the same injection.
- You may give an injection of BYETTA and insulin in the same body area (such as your stomach area), but not right next to each other.
- Change (rotate) your injection sites within the area you chose with each dose. Do not use the same spot for each injection.
- Do not share your BYETTA pen with other people, even if the needle has been changed. You may give other people a serious infection or get a serious infection from them.
- If you take too much BYETTA, call your healthcare provider or Poison Help line at 1-800-222-1222 or go to the nearest hospital emergency room right away.

What are the possible side effects of BYETTA?

BYETTA may cause serious side effects, including:

- See "What is the most important information I should know about BYETTA?"
- low blood sugar (hypoglycemia). Your risk for getting low blood sugar is higher if you take BYETTA with another medicine that can cause low blood sugar, such as a sulfonylurea or insulin.
- Signs and symptoms of low blood sugar may include:
  ∘ dizziness or light-headedness
  ∘ sweating
  ∘ confusion or drowsiness
  ∘ headache
  ∘ blurred vision
  ∘ slurred speech
  ∘ shakiness
  ∘ fast heartbeat
  ∘ anxiety, irritability, or mood changes
  ∘ hunger
  ∘ weakness
- feeling jittery
- dehydration leading to kidney problems. Diarrhea, nausea, and vomiting may cause a loss of fluids (dehydration) which may cause kidney problems. It is important for you to drink fluids to help reduce your chance of dehydration. Tell your healthcare provider right away if you have nausea, vomiting, or diarrhea that does not go away.
- severe stomach problems. Stomach problems, sometimes severe, have been reported in people who use BYETTA. Tell your healthcare provider if you have stomach problems that are severe or will not go away.
- low blood platelet count (drug-induced thrombocytopenia). BYETTA may cause the number of platelets in your blood to be reduced. When your platelet count is too low, your body cannot form blood clots. You could have serious bleeding that could lead to death. Stop using BYETTA and call your healthcare provider right away if you have unusual bleeding or bruising.
- severe allergic reactions. Stop taking BYETTA and get medical help right away if you have any symptom of a severe allergic reaction including:
  ∘ swelling of your face, lips, tongue or throat
  ∘ problems breathing or swallowing
  ∘ severe rash or itching
  ∘ fainting or feeling dizzy
  ∘ very rapid heartbeat
- gallbladder problems. Gallbladder problems have happened in some people who take BYETTA. Tell your healthcare provider right away if you get symptoms of gallbladder problems, which may include:
  ∘ pain in your upper stomach (abdomen)
  ∘ yellowing of skin or eyes (jaundice)
  ∘ fever
  ∘ clay-colored stools
- food or liquid getting into the lungs during surgery or other procedures that use anesthesia or deep sleepiness (deep sedation). BYETTA may increase the chance of food getting into your lungs during surgery or other procedures. Tell all your healthcare providers that you are taking BYETTA before you are scheduled to have surgery or other procedures.

The most common side effects of BYETTA include:

  ∘ nausea
  ∘ feeling jittery
  ∘ indigestion
  ∘ vomiting
  ∘ dizziness
  ∘ constipation
  ∘ diarrhea
  ∘ headache
  ∘ weakness

Talk to your healthcare provider about any side effect that bothers you or that does not go away. These are not all the possible side effects of BYETTA.

Call your doctor for medical advice about side effects. You may report side effects to FDA at 1-800-FDA-1088.

How should I store BYETTA?

- Store your new, unused BYETTA Pen in the original carton in a refrigerator at 36°F to 46°F (2°C to 8°C).
- After first use, keep your BYETTA Pen at a temperature cooler than 77°F (25°C).
- Do not freeze your BYETTA Pen. Do not use BYETTA if it has been frozen.
- Protect BYETTA from light.
- Use a BYETTA Pen for only 30 days. Throw away a used BYETTA Pen after 30 days, even if there is some medicine left in the pen.
- Do not use BYETTA after the expiration date printed on the label.
- Keep your BYETTA Pen, pen needles, and all medicines out of the reach of children.

General information about the safe and effective use of BYETTA.

Medicines are sometimes prescribed for purposes other than those listed in a Medication Guide. Do not use BYETTA for a condition for which it was not prescribed. Do not give BYETTA to other people, even if they have the same symptoms that you have. It may harm them. You can ask your healthcare provider or pharmacist for information about BYETTA that is written for health professionals.

What are the ingredients in BYETTA?

Active ingredient: exenatide

Inactive ingredients: metacresol, mannitol, glacial acetic acid, and sodium acetate trihydrate in water for injection.

BYETTA® is a registered trademark of the AstraZeneca group of companies. All other trademarks are the trademarks of their respective owners.

Distributed by:

AstraZeneca Pharmaceuticals LP

Wilmington, DE 19850

For more information, call 1-800-236-9933.

This Medication Guide has been approved by the U.S. Food and Drug Administration Revised 05/2025

INSTRUCTIONS FOR USE
BYETTA® (bye-A-tuh)

(exenatide) injection

for subcutaneous use

5 mcg /dose, 300 mcg/1.2 mL (250 mcg/mL)

Do not share your BYETTA Pen with other people, even if the needle has been changed. You may give other people a serious infection or get a serious infection from them.

Section 1

Read this section completely before you begin. Then, move on to Section 2–Getting Started.

WHAT YOU NEED TO KNOW ABOUT YOUR BYETTA PEN

INSTRUCTIONS FOR USE

Read these instructions carefully BEFORE using your BYETTA Pen. For complete dosing and safety information, also read the BYETTA Medication Guide that comes with the BYETTA Pen carton.

It is important that you use your pen correctly. Failure to follow these instructions completely may result in a wrong dose, a broken pen or an infection.

These instructions do not take the place of talking with your healthcare provider about your medical condition or your treatment. If you are having problems using your BYETTA Pen, call toll free 1-800-236-9933.

IMPORTANT INFORMATION ABOUT YOUR BYETTA PEN

- Each BYETTA Pen contains enough medicine for injection two times each day for 30 days. You do not have to measure any doses, the pen measures each dose for you.
- Do not mix BYETTA and insulin in the same syringe or vial even if you take them at the same time.
- If any part of your pen appears broken or damaged, do not use the pen.
- This BYETTA Pen is not recommended for use by people who are blind or have vision problems without the help of a person trained in the proper use of the pen.
- Follow the injection method explained to you by your healthcare provider.
- Follow Section 2 only to set up a new pen before first use.
- Section 3 of these Instructions for Use should be used for every injection.

ABOUT PEN NEEDLES

What kinds of needles can be used with my BYETTA Pen?

- Pen needles are not included with your pen. You may need a prescription to get them from your pharmacist.
- Use 29 (thin), 30, or 31 (thinner) gauge disposable pen needles with your BYETTA Pen. Ask your healthcare provider which needle gauge and length is best for you.

Do I use a new needle for each injection?

- Yes. Do not reuse or share your needles with other people. You may give other people a serious infection or get a serious infection from them.
- Remove the needle from the pen immediately after you complete each injection. This will help prevent leakage of BYETTA, keep out air bubbles, reduce needle clogs, and decrease the risk of infection.
- Do not push the injection button on your pen unless a needle is attached to the pen.

How do I throw away my needles?

Put your used needles in a FDA-cleared sharps disposal container right away after use. Do not throw away (dispose of) loose needles and syringes in your household trash. If you do not have a FDA-cleared sharps disposal container, you may use a household container that is:

- Made of a heavy-duty plastic,
- Can be closed with a tight-fitting, puncture-resistant lid, without sharps being able to come out,
- Upright and stable during use,
- Leak-resistant, and
- Properly labeled to warn of hazardous waste inside the container.

When your sharps disposal container is almost full, you will need to follow your community guidelines for the right way to dispose of your sharps disposal container. There may be state or local laws about how you should throw away used needles and syringes.

Do not share your BYETTA Pen with other people, even if the needle has been changed. You may give other people a serious infection or get a serious infection from them.

STORING YOUR BYETTA PEN

How do I store my BYETTA Pen?

- Prior to first use, store your unused BYETTA Pen in the original carton in a refrigerator at 36°F to 46°F (2°C to 8°C).
- After first use, your BYETTA Pen can be kept at a temperature cooler than 77°F (25°C).
- Do not freeze your BYETTA Pen. Do not use BYETTA if it has been frozen. BYETTA should be protected from light.
- When carrying the pen away from home, store the pen at a temperature between 36°F to 77°F (2°C to 25°C) and keep dry.
- Do not store the pen with the needle attached. If the needle is left on the pen, BYETTA may leak from the pen and air bubbles may form in the cartridge.

Keep your pen and needles out of the reach of children.

How long can I use a BYETTA Pen?

- You can use your BYETTA Pen for up to 30 days after setting up a new pen for first use. After 30 days, throw away the BYETTA Pen in a FDA-cleared sharps disposal container, even if it is not completely empty.
- Mark the date when you first used your pen and the date 30 days later in the spaces below:

Date of First Use Date to Throw Away Pen

- BYETTA should not be used after the expiration date printed on the pen label.

How do I clean my BYETTA Pen?

- Wipe the outside of the pen with a clean, damp cloth.
- White particles may appear on the outside tip of the cartridge during normal use. You may remove them with an alcohol wipe or alcohol swab.

See the complete BYETTA Medication Guide that comes with BYETTA. For more information, call toll free 1-800-236-9933.

Section 2

Read and follow the directions in this section only after you've read Section 1—What You Need To Know About Your BYETTA Pen.

GETTING STARTED

Set up your new pen just before you use it the first time. For routine use, do not repeat this one-time-only new pen setup. If you do, you will run out of BYETTA before 30 days of use.

ONE-TIME-ONLY NEW PEN SETUP

STEP A Check the Pen

Note: Small air bubbles in the cartridge are normal.

- Wash hands prior to use.
- Check pen label to make sure it is your 5 mcg pen.
- Pull off the blue pen cap.

- Check BYETTA in the cartridge. The liquid should be clear, colorless, and free of particles. If not, do not use.

STEP B Attach the Needle

- Remove paper tab from outer needle shield.
- Push outer needle shield containing the needle straight onto the pen, then screw needle on until secure.

- Pull off outer needle shield. Do not throw away.

- Pull off inner needle shield and throw away. A small drop of liquid may appear. This is normal.

STEP C Dial the Dose

- Check that the is in the dose window. If not, turn dose knob away from you (clockwise) until it stops and the is in the dose window.

- Pull dose knob out until it stops and the is in the dose window.

- Turn dose knob away from you until it stops at . Make sure that the 5 with the line under it is in the center of the dose window.

Note: If you cannot turn the dose knob away from you to the , see Commonly Asked Questions, number 7, in Section 4 of these Instructions for Use.

STEP D Prepare the Pen

PUSH & HOLD

- Point the needle of the pen up and away from you.

- Use thumb to firmly push injection button in until it stops, then continue holding the injection button in while slowly counting to 5.
- If you do not see a stream or several drops come from the needle tip, repeat Steps C & D.

- Pen preparation is complete when the is in the center of the dose window and you have seen a stream or several drops come from the needle tip.

Note: Each device contains additional volume to allow for troubleshooting the device 4 times.If you do not see liquid after 4 times, see Commonly Asked Questions, number 3, in Section 4 of these Instructions for Use.

STEP E Complete New Pen Setup

- Turn dose knob away from you until it stops and the is in the dose window.

- For routine use, do not repeat this one-time-only new pen setup. If you do, you will run out of BYETTA before 30 days of use.

- You are now ready for your first dose of BYETTA.
- Go to Section 3, Step 3, for instructions on how to inject your first routine dose.

Note: If you cannot turn the dose knob, see Commonly Asked Questions, number 7, in Section 4 of Instructions for Use.

Section 3

Now that you have done the one-time-only new pen setup, follow Section 3 for all of your injections.

ROUTINE USE

STEP 1 Check the Pen

Note: Small air bubbles will not harm you or affect your dose.

- Wash hands prior to use.
- Check pen label to make sure it is your 5 mcg pen.
- Pull off the blue pen cap.

- Check BYETTA in the cartridge.
- The liquid should be clear, colorless, and free of particles. If it is not, do not use.

STEP 2 Attach the Needle

- Remove paper tab from outer needle shield.
- Push outer needle shield containing the needle straight onto pen, then screw needle on until secure.

- Pull off outer needle shield. Do not throw away.

- Pull off inner needle shield and throw away. A small drop of liquid may appear. This is normal.

STEP 3 Dial the Dose

- Check that the is in the dose window. If not, turn dose knob away from you (clockwise) until it stops and the is in the dose window.

- Pull dose knob out until it stops and the is in the dose window.

- Turn dose knob away from you until it stops at . Make sure that the 5 with the line under it is in the center of the dose window.

Note: If you cannot turn the dose knob away from you to the , see Commonly Asked Questions, number 7, in Section 4 of these Instructions for Use.

STEP 4 Inject the Dose

PUSH & HOLD

- Grip pen firmly.
- Insert needle into skin using the under-the-skin (subcutaneous) injection method explained by your healthcare provider.

- Use thumb to firmly push injection button in until it stops. Continue holding in the injection button while slowly counting to 5 to get a full dose.
- Remove needle from skin.

- Injection is complete when the is in the center of the dose window.
- The pen is now ready to reset.

Note: If you see several drops of BYETTA leaking from the needle after the injection, you may not have received a complete dose. See Commonly Asked Questions, number 4, in Section 4 of these Instructions for Use.

STEP 5 Reset the Pen

- Turn dose knob away from you until it stops and the is in the dose window.

Note: If you cannot turn the dose knob, or if your pen leaks, your full dose has not been delivered. See Commonly Asked Questions, numbers 4 and 7, in Section 4 of these Instructions for Use.

STEP 6 Remove and Dispose of the Needle

- Carefully put the outer needle shield back over the needle.
- Remove the needle after each injection.

- Unscrew the needle.

- Throw away needles in a FDA-cleared sharps disposal container (See above “How do I throw away my needles?”) or as recommended by your healthcare provider.

STEP 7 Store Pen for Next Dose

- Replace Blue Pen Cap on pen before storage.
- Store your BYETTA Pen at a temperature between 36°F to 77°F (2°C to 25°C). (See Storing Your BYETTA Pen in Section 1 of these Instructions for Use for complete storage information.)
- When it is time for your next routine dose, go to Section 3, Step 1, and repeat Steps 1–7.

Section 4

COMMONLY ASKED QUESTIONS

1.

Do I need to do the One-Time-Only New Pen Setup before every dose?

- No. The One-Time-Only New Pen Setup is done only once, just before each new pen is used for the first time.
- The purpose of the setup is to make sure that your BYETTA Pen is ready to use for the next 30 days.
- If you repeat the One-Time-Only New Pen Setup before each routine dose, you will not have enough BYETTA for 30 days. The small amount of BYETTA used in the new pen setup will not affect the 30-day supply of BYETTA.

2.

Why are there air bubbles in the cartridge?

- A small air bubble is normal. It will not harm you or affect your dose.
- If the pen is stored with a needle attached, air bubbles may form in the cartridge. Do not store the pen with the needle attached.

3.

What should I do if BYETTA does not come out of the needle tip after four tries during One-Time-Only New Pen Setup?

- Carefully put the outer needle shield back over the needle. Remove the needle by unscrewing it. Throw away the needle properly.
- Attach a new needle and repeat One-Time-Only New Pen Setup, Steps B–E, in Section 2 of these Instructions for Use. Once you see several drops or a stream of liquid coming out of the tip of the needle, the setup is complete.

4.

Why do I see BYETTA leaking from my needle after I have finished my injection?

It is normal for a single drop to remain on the tip of your needle after your injection is complete. If you see more than one drop:

- You may not have received your full dose. Do not inject another dose. Talk with your healthcare provider about what to do about a partial dose.
- To make sure that you get your full dose, when you take your injections, firmly push and hold the injection button in and slowly count to 5 (see Section 3, Step 4: Inject the Dose).

5.

How can I tell when the injection is complete?

The injection is complete when:

- You have firmly pushed the injection button in all the way until it stops

and

- You have slowly counted to 5 while you are still holding the injection button in and the needle is still in your skin

and

- The is in the center of the dose window.

If you hear a click sound from your BYETTA Pen, ignore it. You must follow all the steps listed above to make sure your injection is complete.

6.

Where should I inject BYETTA?

Inject BYETTA into your abdomen, thigh, or upper arm using the injection method explained to you by your healthcare provider.

Change (rotate) your injection sites within the area you choose for each dose. Do not use the same injection site for each injection.

7.

What if I cannot pull, turn, or push the dose knob?

Check the symbol in the dose window. Follow the steps next to the matching symbol.

If is in the dose window:

- Pull the dose knob out until appears.

If is in the dose window and the dose knob will not turn:

- The cartridge in your BYETTA Pen may not have enough medicine to deliver a full dose. A small amount of BYETTA will always stay in the cartridge. If the cartridge contains a small amount and the dose knob will not turn, your pen does not have enough BYETTA and will not deliver any more doses. Get a new BYETTA Pen.

If and part of are in the dose window and the dose knob cannot be pushed in:

- The dose knob was not turned all the way. Continue turning the dose knob away from you until is in the center of the dose window.

If part of and part of are in the dose window and the dose knob cannot be pushed in:

- The needle may be clogged, bent, or incorrectly attached.
- Attach a new needle. Make sure needle is on straight and screwed on all the way.
- Firmly push the injection button in all the way. BYETTA should come from needle tip.

If is in the dose window and the dose knob will not turn:

- The injection button was not pushed in all the way and a complete dose was not delivered. Talk with your healthcare provider about what to do about a partial dose.
- Follow these steps to reset your pen for your next injection:
  ∘ Firmly push the injection button in all the way until it stops. Keep holding the injection button in and slowly count to 5. Then release the injection button and turn the dose knob away from you until appears in the dose window.
  ∘ If you cannot turn the dose knob, the needle may be clogged. Replace the needle and repeat the step above.

- For your next dose, be sure to firmly push and hold the injection button in and slowly count to 5 before removing needle from skin.

See the complete BYETTA Medication Guide that comes with BYETTA. For more information, call toll free 1-800-236-9933.

Distributed by:
AstraZeneca Pharmaceuticals LP
Wilmington, DE 19850

BYETTA® is a registered trademark of the AstraZeneca group of companies.

This Instructions for Use has been approved by the U.S. Food and Drug Administration.

Revised: September 2025

Medication Guide

INSTRUCTIONS FOR USE
BYETTA® (bye-A-tuh)

(exenatide) injection

for subcutaneous use

10 mcg/dose, 600 mcg/ 2.4 ml (250 mcg/mL)

Do not share your BYETTA Pen with other people, even if the needle has been changed. You may give other people a serious infection or get a serious infection from them.

Section 1

Read this section completely before you begin. Then, move on to Section 2−Getting Started.

WHAT YOU NEED TO KNOW ABOUT YOUR BYETTA PEN

PEN INSTRUCTIONS FOR USE

Read these instructions carefully BEFORE using your BYETTA Pen. For complete dosing and safety information, also read the BYETTA Medication Guide that comes with the BYETTA Pen carton.

It is important that you use your pen correctly. Failure to follow these instructions completely may result in a wrong dose, a broken pen or an infection.

These instructions do not take the place of talking with your healthcare provider about your medical condition or your treatment. If you are having problems using your BYETTA Pen, call toll free 1-800-236-9933.

IMPORTANT INFORMATION ABOUT YOUR BYETTA PEN

- Each BYETTA Pen contains enough medicine for injection two times each day for 30 days. You do not have to measure any doses, the pen measures each dose for you.
- Do not mix BYETTA and insulin in the same syringe or vial even if you take them at the same time.
- If any part of your pen appears broken or damaged, do not use the pen.
- This BYETTA Pen is not recommended for use by people who are blind or have vision problems without the help of a person trained in the proper use of the pen.
- Follow the injection method explained to you by your healthcare provider.
- Follow Section 2 only to set up a new pen before first use.
- Section 3 of these Instructions for Use should be used for every injection.

ABOUT PEN NEEDLES

What kinds of needles can be used with my BYETTA Pen?

- Pen needles are not included with your pen. You may need a prescription to get them from your pharmacist.
- Use 29 (thin), 30, or 31 (thinner) gauge disposable pen needles with your BYETTA Pen. Ask your healthcare provider which needle gauge and length is best for you.

Do I use a new needle for each injection?

- Yes. Do not reuse or share your needles with other people. You may give other people a serious infection or get a serious infection from them.
- Remove the needle from the pen immediately after you complete each injection. This will help prevent leakage of BYETTA, keep out air bubbles, reduce needle clogs, and decrease the risk of infection.
- Do not push the injection button on your pen unless a needle is attached to the pen.

How do I throw away my needles?

Put your used needles in a FDA-cleared sharps disposal container right away after use. Do not throw away (dispose of) loose needles and syringes in your household trash. If you do not have a FDA-cleared sharps disposal container, you may use a household container that is:

- Made of a heavy-duty plastic,
- Can be closed with a tight-fitting, puncture-resistant lid, without sharps being able to come out,
- Upright and stable during use,
- Leak-resistant, and
- Properly labeled to warn of hazardous waste inside the container.

When your sharps disposal container is almost full, you will need to follow your community guidelines for the right way to dispose of your sharps disposal container. There may be state or local laws about how you should throw away used needles and syringes.

Do not share your BYETTA Pen with other people, even if the needle has been changed. You may give other people a serious infection or get a serious infection from them.

STORING YOUR BYETTA PEN

How do I store my BYETTA Pen?

- Prior to first use, store your unused BYETTA Pen in the original carton in a refrigerator at 36°F to 46°F (2°C to 8°C).
- After first use, your BYETTA Pen can be kept at a temperature cooler than 77°F (25°C).
- Do not freeze your BYETTA Pen. Do not use BYETTA if it has been frozen. BYETTA should be protected from light.
- When carrying the pen away from home, store the pen at a temperature between 36°F to 77°F (2°C to 25°C) and keep dry.
- Do not store the pen with the needle attached. If the needle is left on the pen, BYETTA may leak from the pen and air bubbles may form in the cartridge.

Keep your pen and needles out of the reach of children.

How long can I use a BYETTA Pen?

- You can use your BYETTA Pen for up to 30 days after setting up a new pen for first use. After 30 days, throw away the BYETTA Pen in a FDA-cleared sharps disposal container, even if it is not completely empty.
- Mark the date when you first used your pen and the date 30 days later in the spaces below:

Date of First Use Date to Throw Away Pen

- BYETTA should not be used after the expiration date printed on the pen label.

How do I clean my BYETTA Pen?

- Wipe the outside of the pen with a clean, damp cloth.
- White particles may appear on the outside tip of the cartridge during normal use. You may remove them with an alcohol wipe or alcohol swab.

See the complete BYETTA Medication Guide that comes with BYETTA. For more information, call toll free 1-800-236-9933.

Section 2

Read and follow the directions in this section only after you've read Section 1—What You Need To Know About Your BYETTA Pen.

GETTING STARTED

Set up your new pen just before you use it the first time. For routine use, do not repeat this one-time-only new pen setup. If you do, you will run out of BYETTA before 30 days of use.

ONE-TIME-ONLY NEW PEN SETUP

STEP A Check the Pen

Note: Small air bubbles in the cartridge are normal.

- Wash hands prior to use.
- Check pen label to make sure it is your 10 mcg pen.
- Pull off the blue pen cap.

- Check BYETTA in the cartridge. The liquid should be clear, colorless, and free of particles. If not, do not use.

STEP B Attach the Needle

- Remove paper tab from outer needle shield.
- Push outer needle shield containing the needle straight onto the pen, then screw needle on until secure.

- Pull off outer needle shield. Do not throw away.

- Pull off inner needle shield and throw away. A small drop of liquid may appear. This is normal.

STEP C Dial the Dose

- Check that the is in the dose window. If not, turn dose knob away from you (clockwise) until it stops and the is in the dose window.

- Pull dose knob out until it stops and the is in the dose window.

- Turn dose knob away from you until it stops at . Make sure that the 10 with the line under it is in the center of the dose window.

Note: If you cannot turn the dose knob away from you to the , see Commonly Asked Questions, number 7, in Section 4 of these Instructions for Use.

STEP D Prepare the Pen

PUSH & HOLD

- Point the needle of the pen up and away from you.

- Use thumb to firmly push injection button in until it stops, then continue holding the injection button in while slowly counting to 5.
- If you do not see a stream or several drops come from the needle tip, repeat Steps C & D.

- Pen preparation is complete when the is in the center of the dose window and you have seen a stream or several drops come from the needle tip.

Note: Each device contains additional volume to allow for troubleshooting the device 4 times. If you do not see liquid after 4 times, see Commonly Asked Questions, number 3, in Section 4 of these Instructions for Use.

STEP E Complete New Pen Setup

- Turn dose knob away from you until it stops and the is in the dose window.

- For routine use, do not repeat this one-time-only new pen setup. If you do, you will run out of BYETTA before 30 days of use.

- You are now ready for your first dose of BYETTA.
- Go to Section 3, Step 3, for instructions on how to inject your first routine dose.

Note: If you cannot turn the dose knob, see Commonly Asked Questions, number 7, in Section 4 of these Instructions for Use.

Section 3

Now that you have done the one-time-only new pen setup, follow Section 3 for all of your injections.

ROUTINE USE

STEP 1 Check the Pen

Note: Small air bubbles will not harm you or affect your dose.

- Wash hands prior to use.
- Check pen label to make sure it is your 10 mcg pen.
- Pull off the blue pen cap.

- Check BYETTA in the cartridge.
- The liquid should be clear, colorless, and free of particles. If it is not, do not use.

STEP 2 Attach the Needle

- Remove paper tab from outer needle shield.
- Push outer needle shield containing the needle straight onto pen, then screw needle on until secure.

- Pull off outer needle shield. Do not throw away.

- Pull off inner needle shield and throw away. A small drop of liquid may appear. This is normal.

STEP 3 Dial the Dose

- Check that the is in the dose window. If not, turn dose knob away from you (clockwise) until it stops and the is in the dose window.

- Pull dose knob out until it stops and the is in the dose window.

- Turn dose knob away from you until it stops at . Make sure that the 10 with the line under it is in the center of the dose window.

Note: If you cannot turn the dose knob away from you to the , see Commonly Asked Questions, number 7, in Section 4 of these Instructions for Use.

STEP 4 Inject the Dose

PUSH & HOLD

- Grip pen firmly.
- Insert needle into skin using the under-the-skin (subcutaneous) injection method explained by your healthcare provider.

- Use thumb to firmly push injection button in until it stops. Continue holding in the injection button while slowly counting to 5 to get a full dose.
- Remove needle from skin.

- Injection is complete when the is in the center of the dose window.
- The pen is now ready to reset.

Note: If you see several drops of BYETTA leaking from the needle after the injection, you may not have received a complete dose. See Commonly Asked Questions, number 4, in Section 4 of these Instructions for Use.

STEP 5 Reset the Pen

- Turn dose knob away from you until it stops and the is in the dose window.

Note: If you cannot turn the dose knob, or if your pen leaks, your full dose has not been delivered. See Commonly Asked Questions, numbers 4 and 7, in Section 4 of these Instructions for Use.

STEP 6 Remove and Dispose of the Needle

- Carefully put the outer needle shield back over the needle.
- Remove the needle after each injection.

- Unscrew the needle.

- Throw away needles in a FDA-cleared sharps disposal container (See above “How do I throw needles?”) or as recommended by your healthcare provider.

STEP 7 Store Pen for Next Dose

- Replace Blue Pen Cap on pen before storage.
- Store your BYETTA Pen at a temperature between 36°F to 77°F (2°C to 25°C). (See Storing Your BYETTA Pen in Section 1 of these Instructions for Use for complete storage information.)
- When it is time for your next routine dose, go to Section 3, Step 1, and repeat Steps 1–7.

Section 4

COMMONLY ASKED QUESTIONS

1.

Do I need to do the One-Time-Only New Pen Setup before every dose?

- No. The One-Time-Only New Pen Setup is done only once, just before each new pen is used for the first time.
- The purpose of the setup is to make sure that your BYETTA Pen is ready to use for the next 30 days.
- If you repeat the One-Time-Only New Pen Setup before each routine dose, you will not have enough BYETTA for 30 days. The small amount of BYETTA used in the new pen setup will not affect the 30-day supply of BYETTA.

2.

Why are there air bubbles in the cartridge?

- A small air bubble is normal. It will not harm you or affect your dose.
- If the pen is stored with a needle attached, air bubbles may form in the cartridge. Do not store the pen with the needle attached.

3.

What should I do if BYETTA does not come out of the needle tip after four tries during One-Time-Only New Pen Setup?

- Carefully put the outer needle shield back over the needle. Remove the needle by unscrewing it. Throw away the needle properly.
- Attach a new needle and repeat One-Time-Only New Pen Setup, Steps B–E, in Section 2 of these Instructions for Use. Once you see several drops or a stream of liquid coming out of the tip of the needle, the setup is complete.

4.

Why do I see BYETTA leaking from my needle after I have finished my injection?

It is normal for a single drop to remain on the tip of your needle after your injection is complete. If you see more than one drop:

- You may not have received your full dose. Do not inject another dose. Talk with your healthcare provider about what to do about a partial dose.
- To make sure that you get your full dose, when you take your injections, firmly push and hold the injection button in and slowly count to 5 (see Section 3, Step 4: Inject the Dose).

5.

How can I tell when the injection is complete?

The injection is complete when:

- You have firmly pushed the injection button in all the way until it stops

and

- You have slowly counted to 5 while you are still holding the injection button in and the needle is still in your skin

and

- The is in the center of the dose window.

If you hear a click sound from your BYETTA Pen, ignore it. You must follow all the steps listed above to make sure your injection is complete.

6.

Where should I inject BYETTA?

Inject BYETTA into your abdomen, thigh, or upper arm using the injection method explained to you by your healthcare provider.

Change (rotate) your injection sites within the area you choose for each dose. Do not use the same injection site for each injection.

7.

What if I cannot pull, turn, or push the dose knob?

Check the symbol in the dose window. Follow the steps next to the matching symbol.

If is in the dose window:

- Pull the dose knob out until appears.

If is in the dose window and the dose knob will not turn:

- The cartridge in your BYETTA Pen may not have enough medicine to deliver a full dose. A small amount of BYETTA will always stay in the cartridge. If the cartridge contains a small amount and the dose knob will not turn, your pen does not have enough BYETTA and will not deliver any more doses. Obtain a new BYETTA Pen.

If and part of are in the dose window and the dose knob cannot be pushed in:

- The dose knob was not turned all the way. Continue turning the dose knob away from you until is in the center of the dose window.

If part of and part of are in the dose window and the dose knob cannot be pushed in:

- The needle may be clogged, bent, or incorrectly attached.
- Attach a new needle. Make sure needle is on straight and screwed on all the way.
- Firmly push the injection button in all the way. BYETTA should come from needle tip.

If is in the dose window and the dose knob will not turn:

- The injection button was not pushed in all the way and a complete dose was not delivered. Talk with your healthcare provider about what to do about a partial dose.
- Follow these steps to reset your pen for your next injection:
  ∘ Firmly push the injection button in all the way until it stops. Keep holding the injection button in and slowly count to 5. Then release the injection button and turn the dose knob away from you until appears in the dose window.
  ∘ If you cannot turn the dose knob, the needle may be clogged. Replace the needle and repeat the step above.

- For your next dose, be sure to firmly push and hold the injection button in and slowly count to 5 before removing needle from skin.

See the complete BYETTA Medication Guide that comes with BYETTA. For more information, call toll free 1-800-236-9933.

Distributed by:
AstraZeneca Pharmaceuticals LP
Wilmington, DE 19850

BYETTA® is a registered trademark of the AstraZeneca group of companies.

This Instructions for Use has been approved by the U.S. Food and Drug Administration

Revised: September 2025

Package/Label Display Panel – 5 mcg

5 mcg per dose

NDC 0310-6512-01

Byetta® exenatide injection

250 mcg/mL, 1.2 mL

Dispense the enclosed Medication Guide to each patient

For Single Patient Use Only

Each prefilled pen will deliver 60 subcutaneous doses, 5 mcg per dose

Rx only

SUBCUTANEOUS USE ONLY
REFRIGERATE – DO NOT FREEZE

DO NOT TRANSFER THIS MEDICATION TO A SYRINGE

Pen needles not included

Ask your healthcare provider which pen needle length and gauge is best for you
Use 29 (thin), 30, or 31 (thinner) gauge disposable pen needles

AstraZeneca

Package/Label Display Panel – 10 mcg

10 mcg per dose

NDC 0310-6524-01

Byetta® exenatide injection

250 mcg/mL, 2.4 mL

Dispense the enclosed Medication Guide to each patient

For Single Patient Use Only

Each prefilled pen will deliver 60 subcutaneous doses, 10 mcg per dose

Rx only

SUBCUTANEOUS USE ONLY
REFRIGERATE – DO NOT FREEZE

DO NOT TRANSFER THIS MEDICATION TO A SYRINGE

Pen needles not included

Ask your healthcare provider which pen needle length and gauge is best for you
Use 29 (thin), 30, or 31 (thinner) gauge disposable pen needles

AstraZeneca